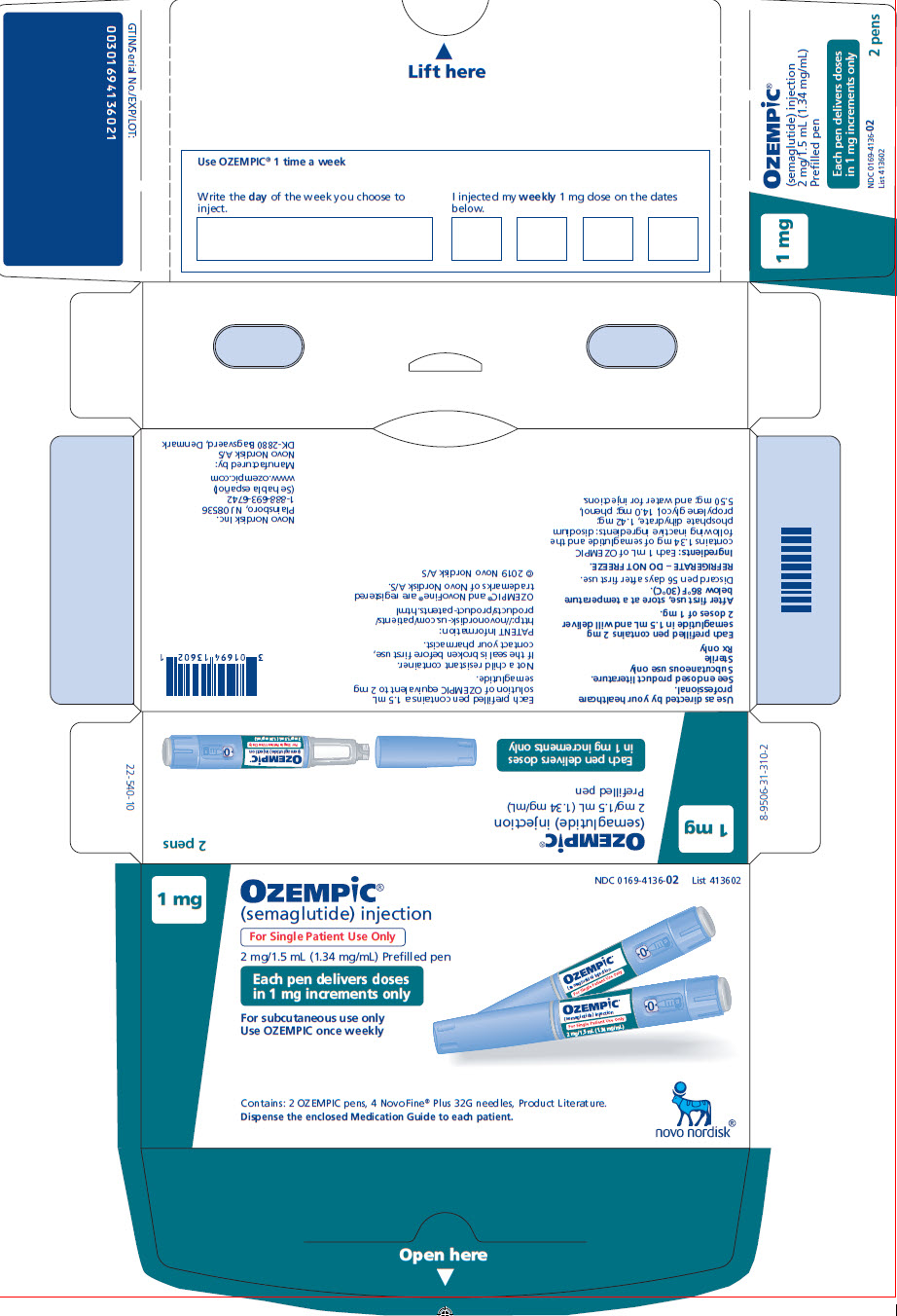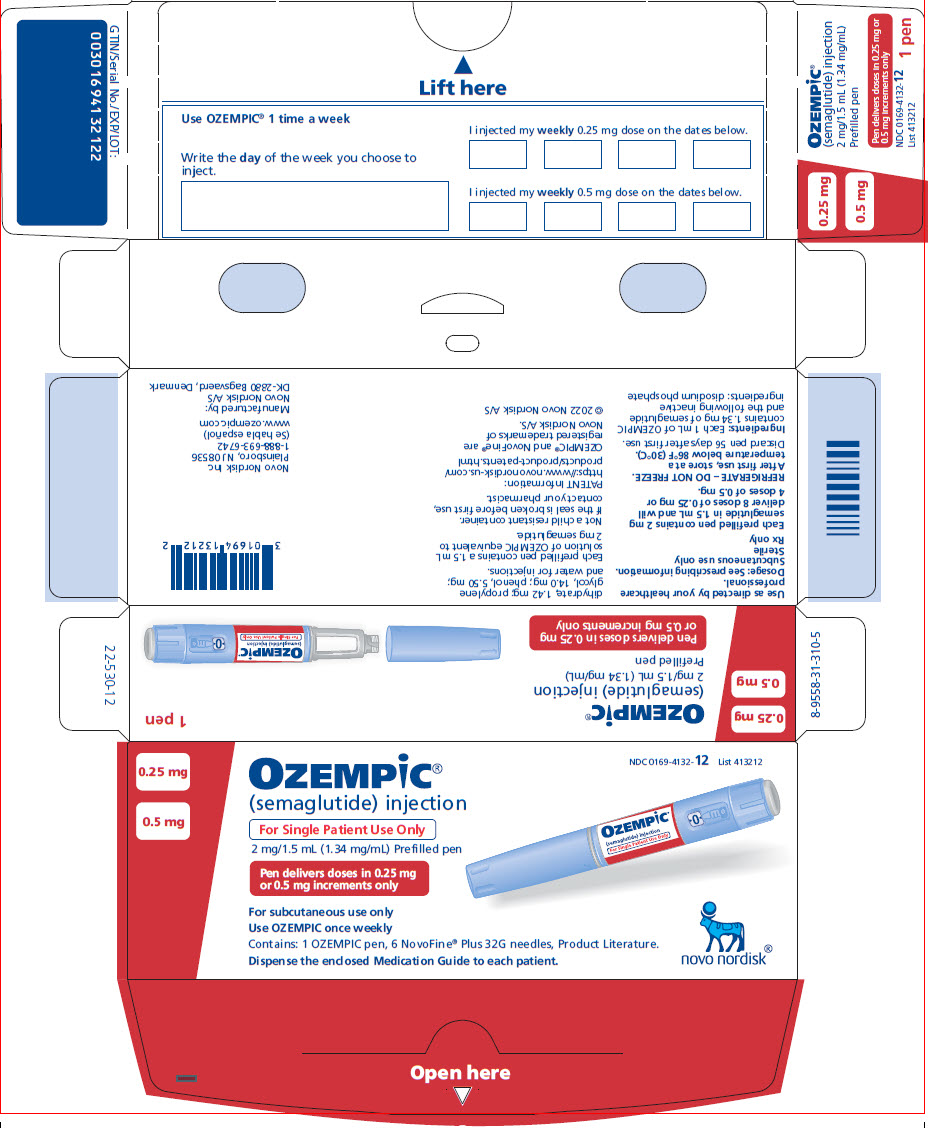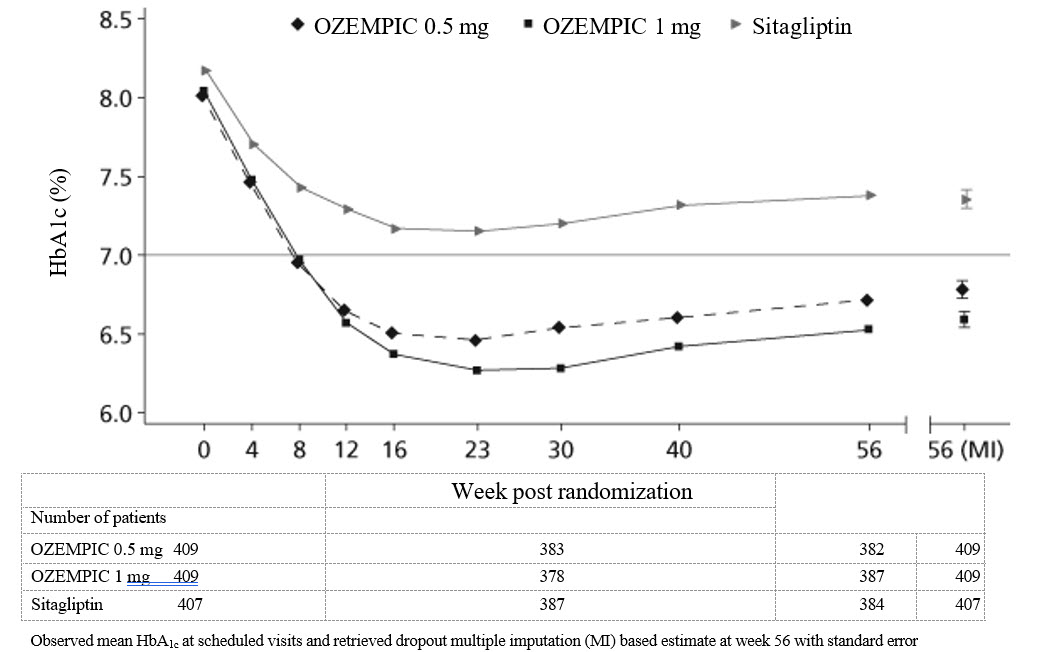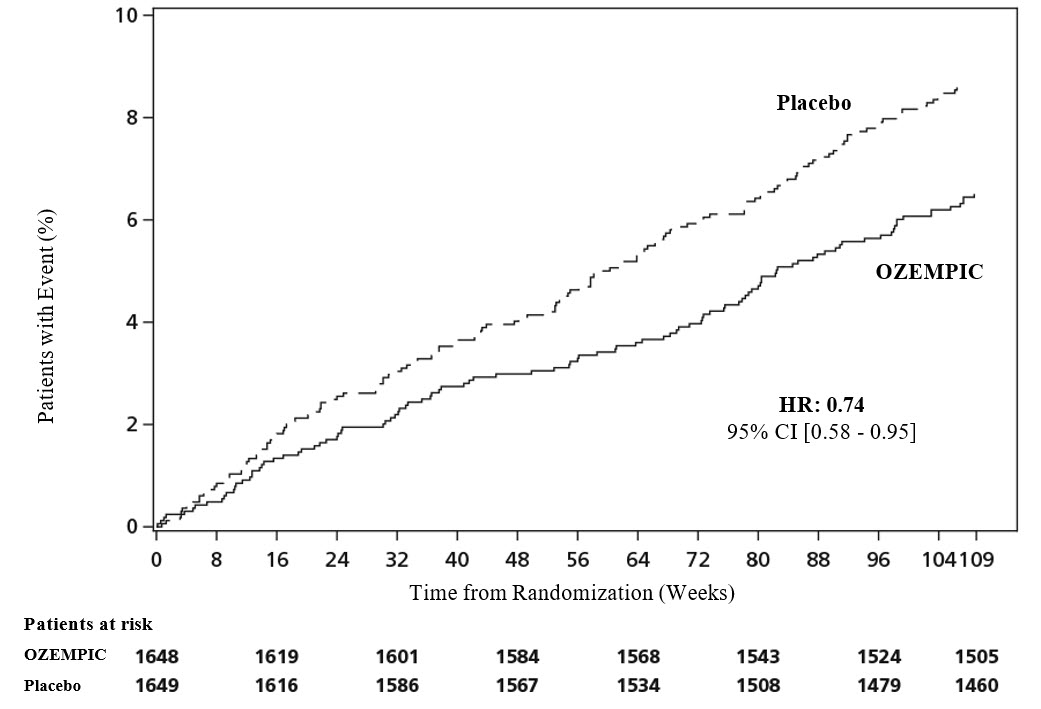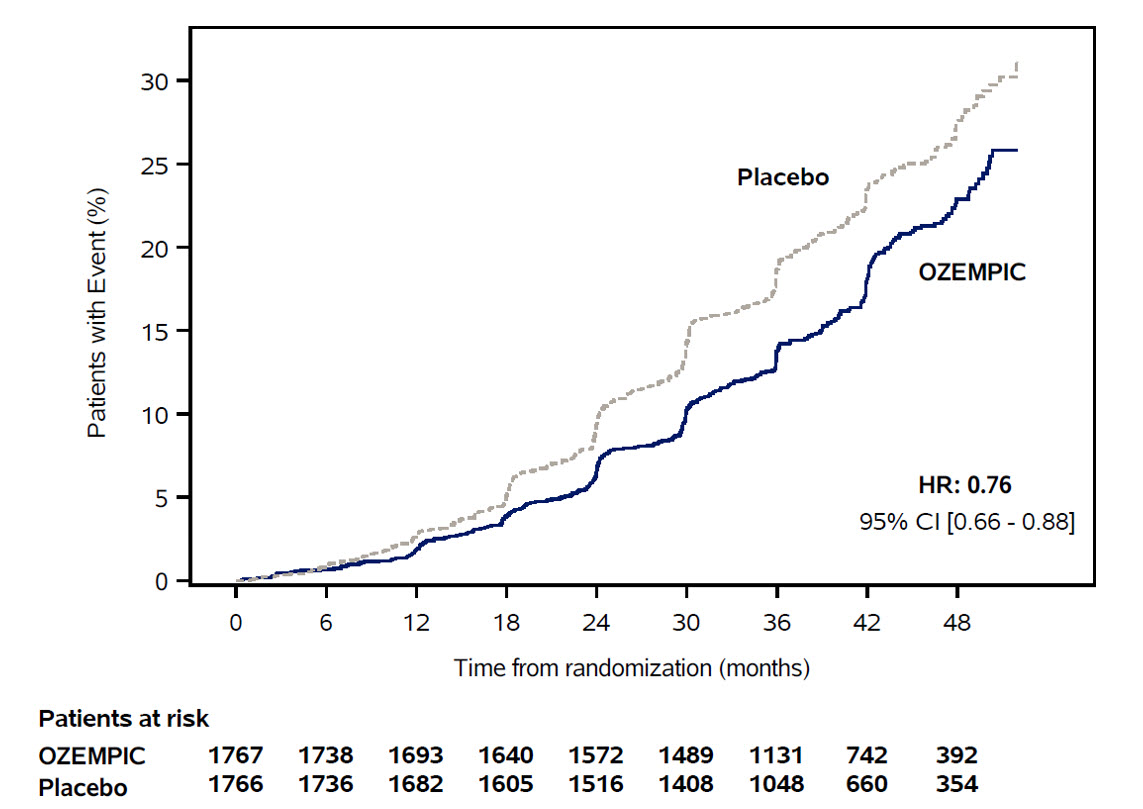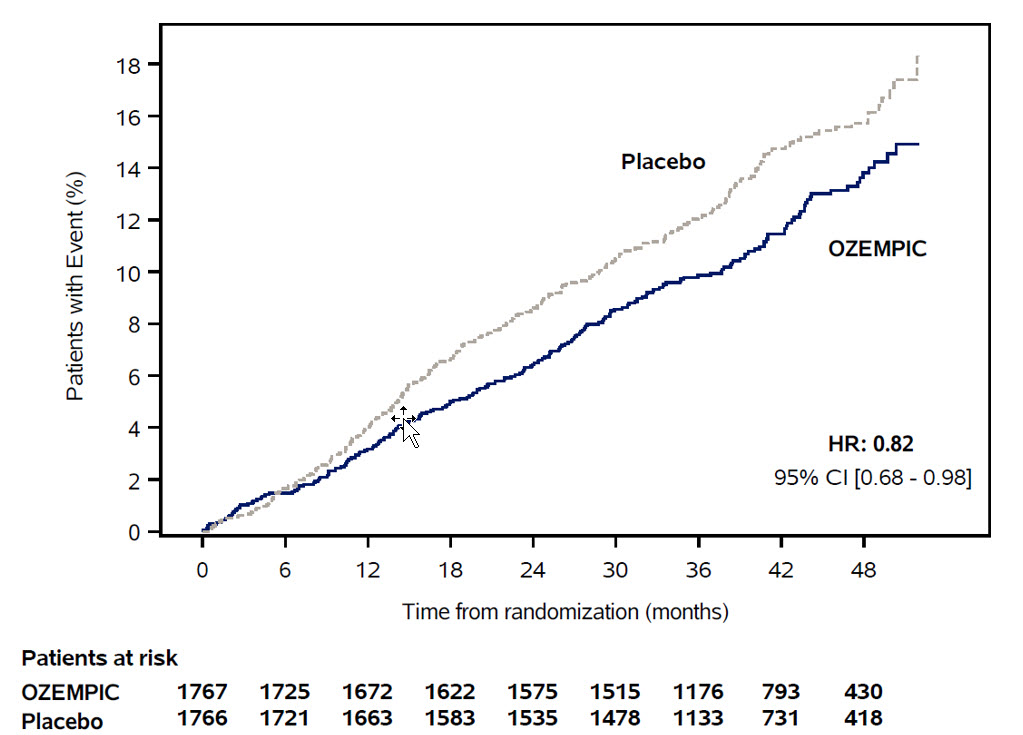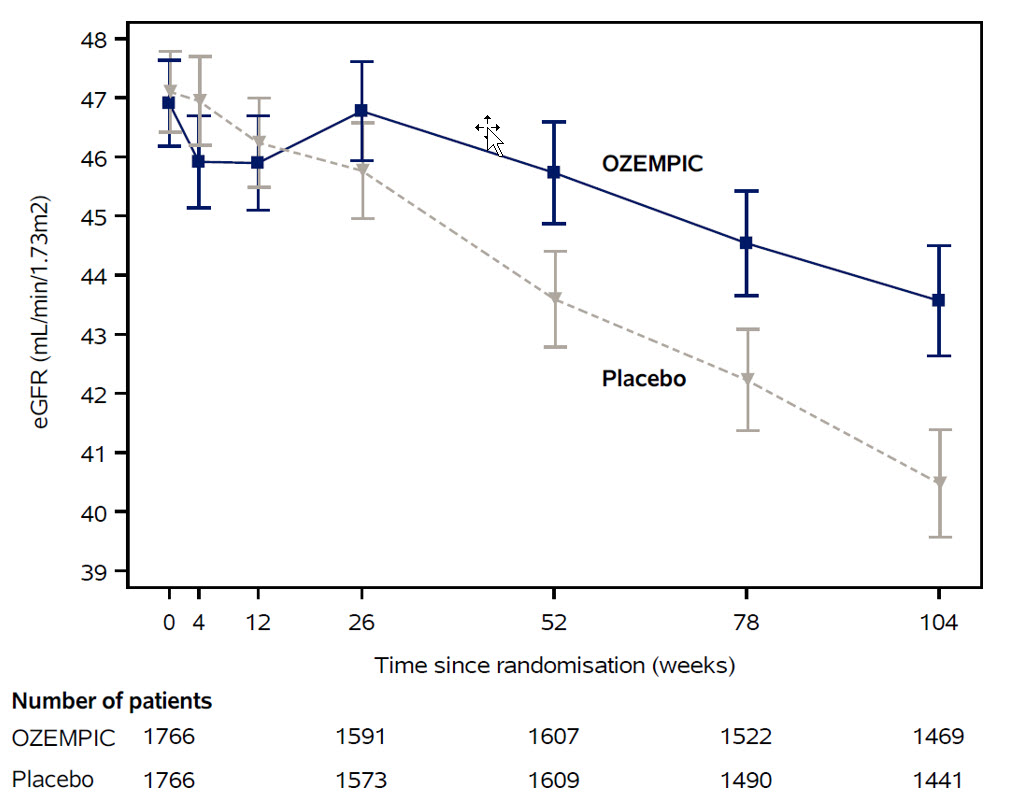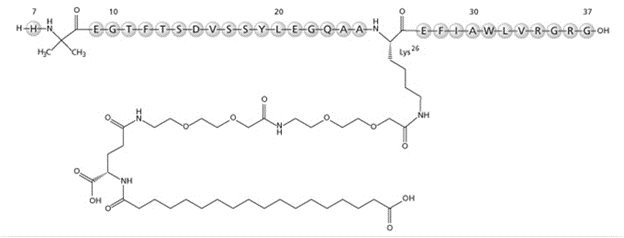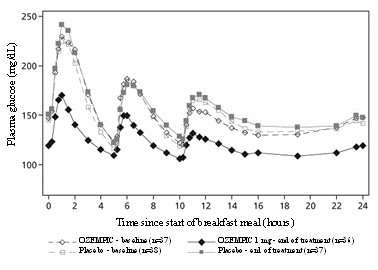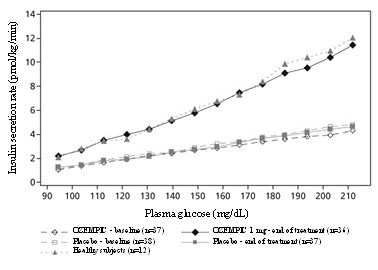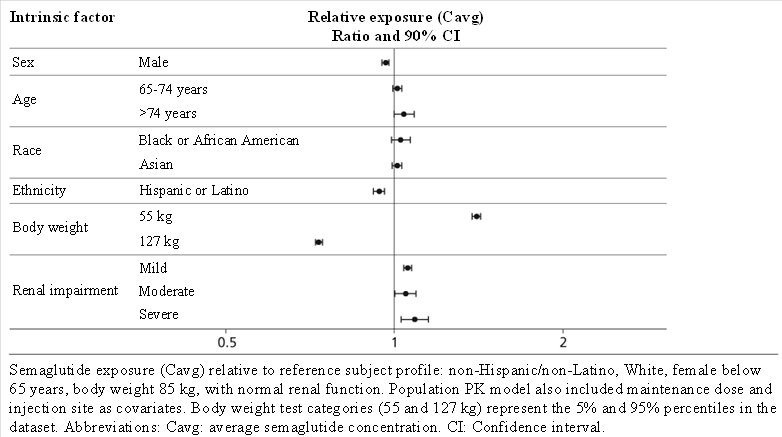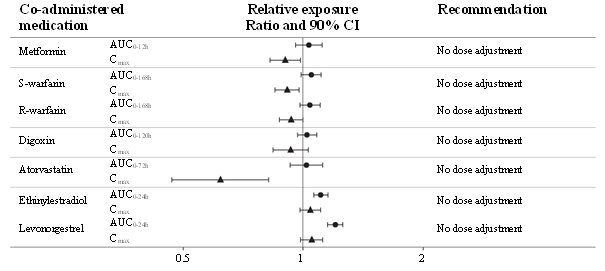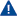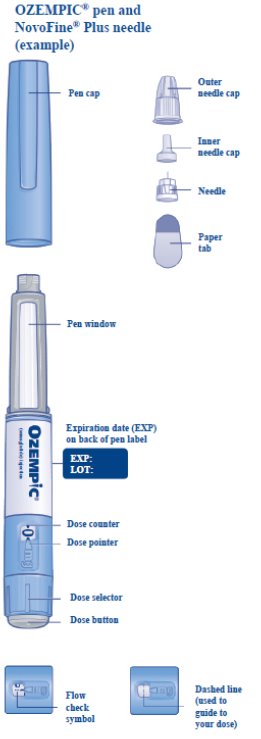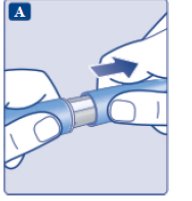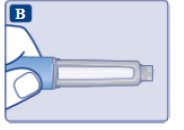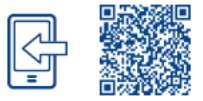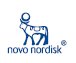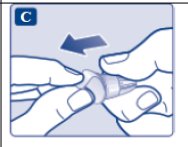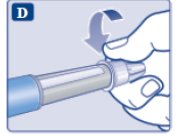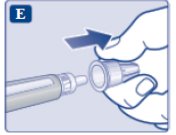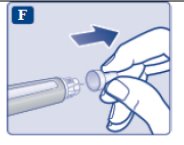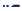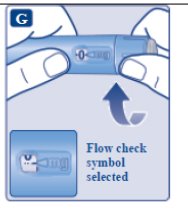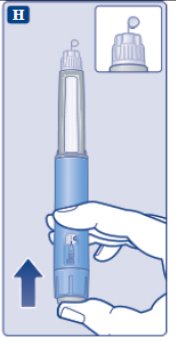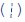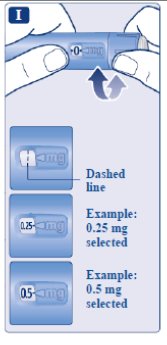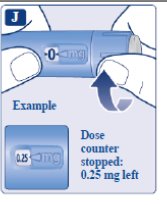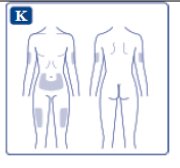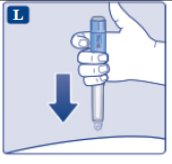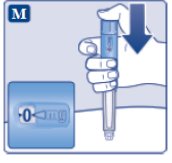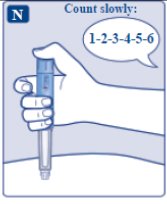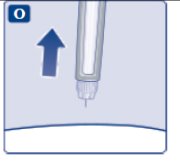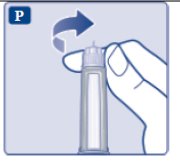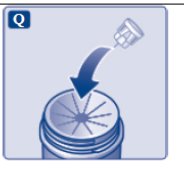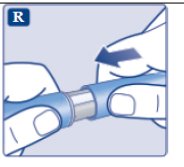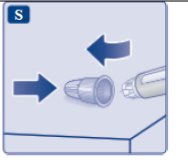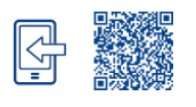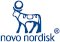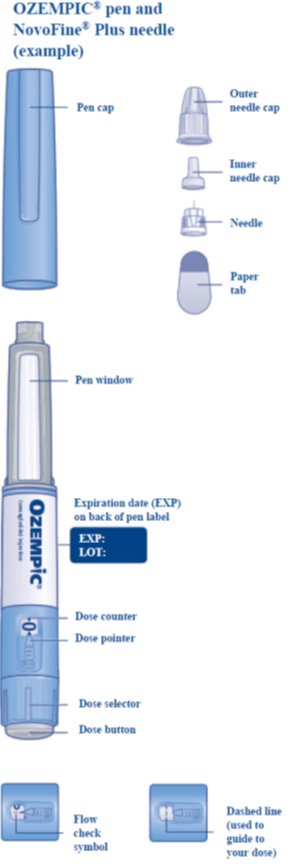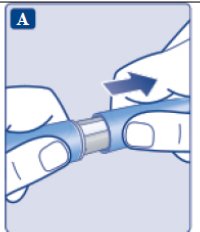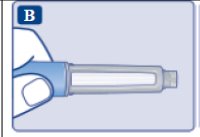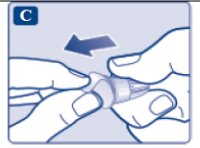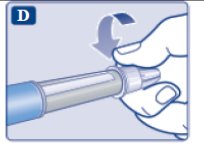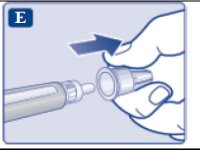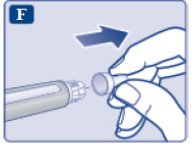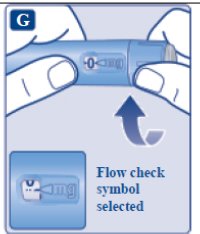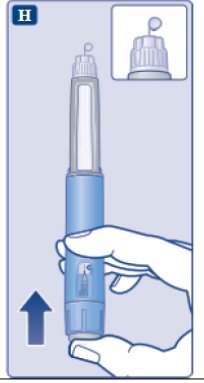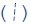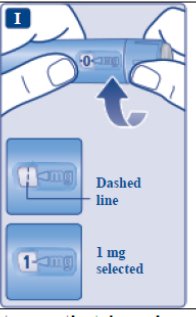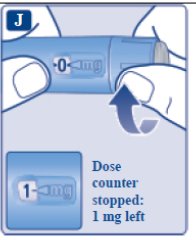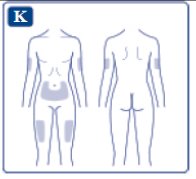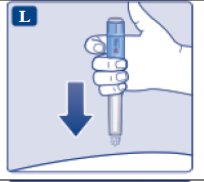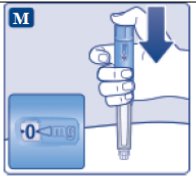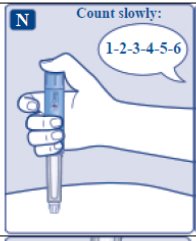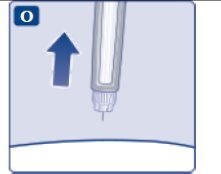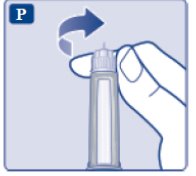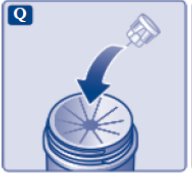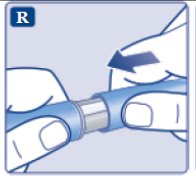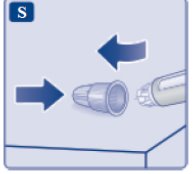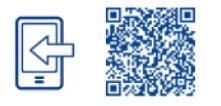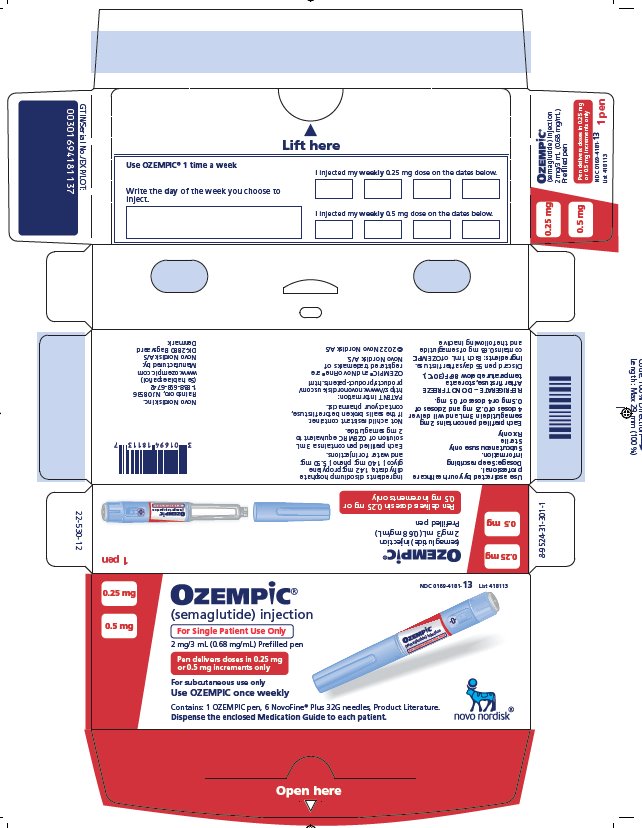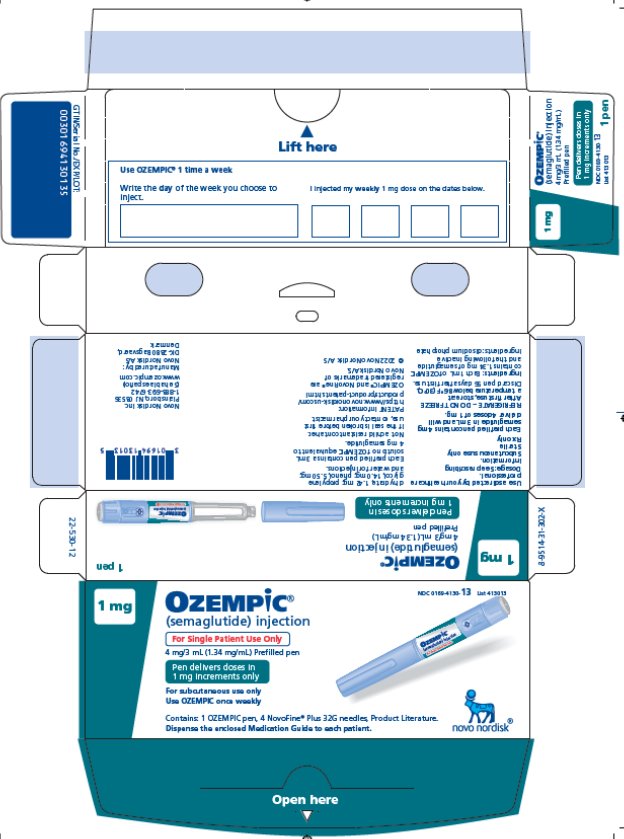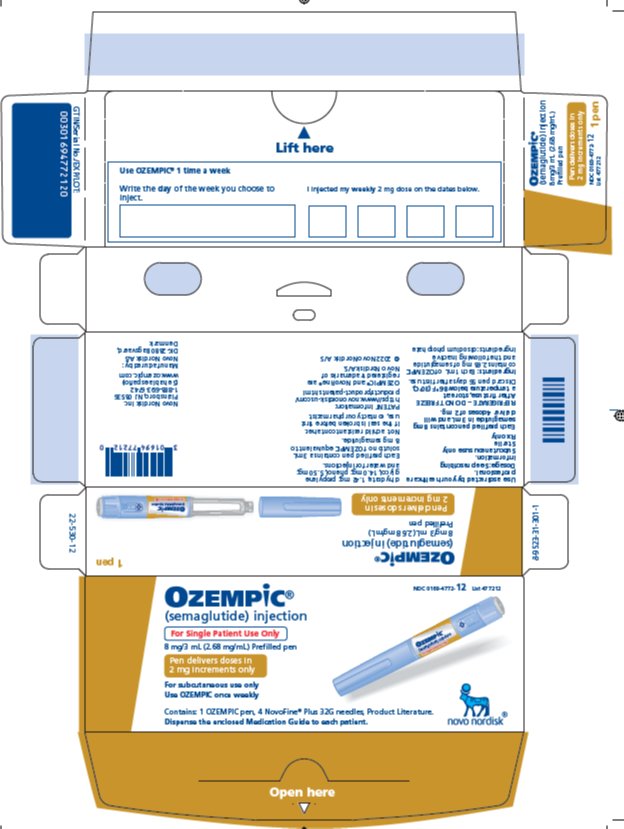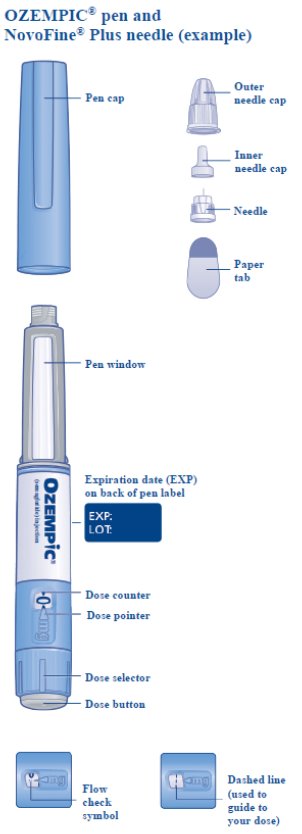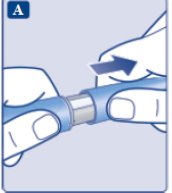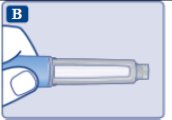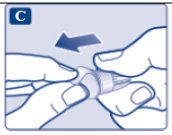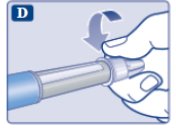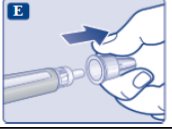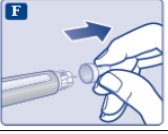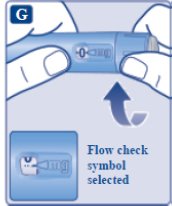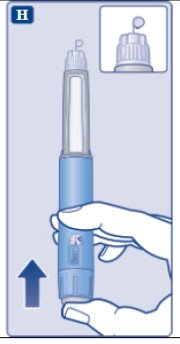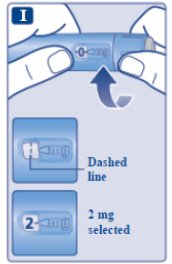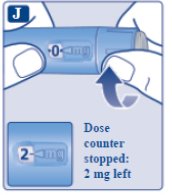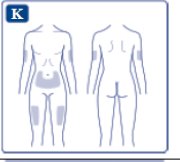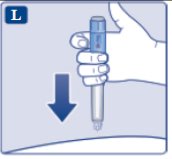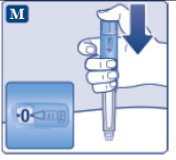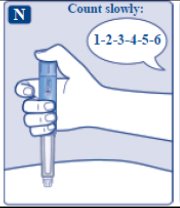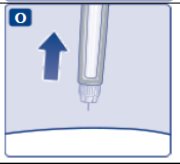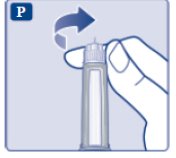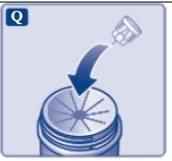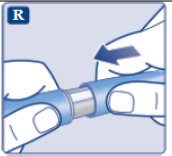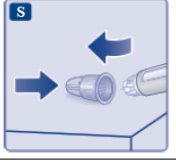 DRUG LABEL: Ozempic
NDC: 0169-4136 | Form: INJECTION, SOLUTION
Manufacturer: Novo Nordisk
Category: prescription | Type: HUMAN PRESCRIPTION DRUG LABEL
Date: 20251014

ACTIVE INGREDIENTS: SEMAGLUTIDE 1.34 mg/1 mL
INACTIVE INGREDIENTS: SODIUM PHOSPHATE, DIBASIC, DIHYDRATE 1.42 mg/1 mL; PROPYLENE GLYCOL 14.0 mg/1 mL; PHENOL 5.50 mg/1 mL; WATER

HIGHLIGHTS OF PRESCRIBING INFORMATION

These highlights do not include all the information needed to use OZEMPIC® safely and effectively. See full prescribing information for OZEMPIC.
OZEMPIC (semaglutide) injection, for subcutaneous use
Initial U.S. Approval: 2017

RECENT MAJOR CHANGES

Indication and Usage (1) …………………………………………… 1/2025

Dosage and Administration (2.2) ………………………......………. 1/2025

Warnings and Precautions,

Severe Gastrointestinal Adverse Reactions (5.7) ………...……10/2025
Pulmonary Aspiration During General Anesthesia or Deep
Sedation (5.10) …………………………….…....……………….1/2025

WARNING: RISK OF THYROID C-CELL TUMORS

See full prescribing information for complete boxed warning.

- In rodents, semaglutide causes thyroid C-cell tumors. It is unknown whether OZEMPIC causes thyroid C-cell tumors, including medullary thyroid carcinoma (MTC), in humans as the human relevance of semaglutide-induced rodent thyroid C-cell tumors has not been determined (5.1, 13.1).
- OZEMPIC is contraindicated in patients with a personal or family history of MTC or in patients with Multiple Endocrine Neoplasia syndrome type 2 (MEN 2). Counsel patients regarding the potential risk of MTC and symptoms of thyroid tumors (4, 5.1).

1 INDICATIONS AND USAGE

OZEMPIC is a glucagon-like peptide 1 (GLP-1) receptor agonist indicated:

- as an adjunct to diet and exercise to improve glycemic control in adults with type 2 diabetes mellitus. (1)
- to reduce the risk of major adverse cardiovascular events in adults with type 2 diabetes mellitus and established cardiovascular disease. (1)
- to reduce the risk of sustained eGFR decline, end-stage kidney disease and cardiovascular death in adults with type 2 diabetes mellitus and chronic kidney disease. (1)

2 DOSAGE AND ADMINISTRATION

- Administer once weekly at any time of day, with or without meals. (2.1)
- Start at 0.25 mg once weekly. After 4 weeks, increase the dosage to 0.5 mg once weekly. (2.2)
- If additional glycemic control is needed, increase the dosage to 1 mg once weekly after at least 4 weeks on the 0.5 mg dose. (2.2)
- If additional glycemic control is needed, increase the dosage to 2 mg once weekly after at least 4 weeks on the 1 mg dosage. (2.2)
- To reduce the risk of sustained eGFR decline, end-stage kidney disease and cardiovascular death, increase the dosage to 1 mg once weekly after at least 4 weeks on the 0.5 mg dosage. (1, 2.2)
- If a dose is missed, administer within 5 days of missed dose. (2.1)
- Inject subcutaneously in the abdomen, thigh, or upper arm. (2.1)

3 DOSAGE FORMS AND STRENGTHS

Injection: 2 mg/3 mL (0.68 mg/mL) available in:

- Single-patient-use pen that delivers 0.25 mg or 0.5 mg per injection (3)

Injection: 4 mg/3 mL (1.34 mg/mL) available in:

- Single-patient-use pen that delivers 1 mg per injection (3)

Injection: 8 mg/3 mL (2.68 mg/mL) available in:

- Single-patient-use pen that delivers 2 mg per injection (3)

4 CONTRAINDICATIONS

- Personal or family history of MTC or in patients with MEN 2. (4)
- Serious hypersensitivity reaction to semaglutide or any of the excipients in OZEMPIC. (4)

5 WARNINGS AND PRECAUTIONS

- Acute Pancreatitis: Has been observed in patients treated with GLP-1 receptor agonists, including semaglutide. Discontinue if pancreatitis is suspected. (5.2)
- Diabetic Retinopathy Complications: Has been reported in a clinical trial. Patients with a history of diabetic retinopathy should be monitored. (5.3)
- Never share an OZEMPIC pen between patients, even if the needle is changed. (5.4)
- Hypoglycemia: Concomitant use with an insulin secretagogue or insulin may increase the risk of hypoglycemia, including severe hypoglycemia. Reducing dose of insulin secretagogue or insulin may be necessary. (5.5)
- Acute Kidney Injury Due to Volume Depletion: Monitor renal function in patients reporting adverse reactions that could lead to volume depletion. (5.6)
- Severe Gastrointestinal Adverse Reactions: Use has been associated with gastrointestinal adverse reactions, sometimes severe. OZEMPIC is not recommended in patients with severe gastroparesis. (5.7)
- Hypersensitivity Reactions: Serious hypersensitivity reactions (e.g., anaphylaxis and angioedema) have been reported. Discontinue OZEMPIC if suspected and promptly seek medical advice. (5.8)
- Acute Gallbladder Disease: If cholelithiasis or cholecystitis are suspected, gallbladder studies are indicated. (5.9)
- Pulmonary Aspiration During General Anesthesia or Deep Sedation: Has been reported in patients receiving GLP-1 receptor agonists undergoing elective surgeries or procedures. Instruct patients to inform healthcare providers of any planned surgeries or procedures. (5.10)

6 ADVERSE REACTIONS

The most common adverse reactions, reported in ≥5% of patients treated with OZEMPIC are: nausea, vomiting, diarrhea, abdominal pain and constipation. (6.1)

To report SUSPECTED ADVERSE REACTIONS, contact Novo Nordisk Inc., at 1-888-693-6742 or FDA at 1-800-FDA-1088 or www.fda.gov/medwatch.

7 DRUG INTERACTIONS

Oral Medications: OZEMPIC delays gastric emptying. May impact absorption of concomitantly administered oral medications. Use with caution. (7.2)

8 USE IN SPECIFIC POPULATIONS

Females and Males of Reproductive Potential: Discontinue OZEMPIC in women at least 2 months before a planned pregnancy due to the long washout period for semaglutide. (8.3)

FULL PRESCRIBING INFORMATION

WARNING: RISK OF THYROID C-CELL TUMORS

- In rodents, semaglutide causes dose-dependent and treatment-duration-dependent thyroid C-cell tumors at clinically relevant exposures. It is unknown whether OZEMPIC causes thyroid C-cell tumors, including medullary thyroid carcinoma (MTC), in humans as human relevance of semaglutide-induced rodent thyroid C-cell tumors has not been determined [see Warnings and Precautions (5.1), Nonclinical Toxicology (13.1)].
- OZEMPIC is contraindicated in patients with a personal or family history of MTC or in patients with Multiple Endocrine Neoplasia syndrome type 2 (MEN 2) [see Contraindications (4)]. Counsel patients regarding the potential risk for MTC with the use of OZEMPIC and inform them of symptoms of thyroid tumors (e.g., a mass in the neck, dysphagia, dyspnea, persistent hoarseness). Routine monitoring of serum calcitonin or using thyroid ultrasound is of uncertain value for early detection of MTC in patients treated with OZEMPIC [see Contraindications (4), Warnings and Precautions (5.1)].

1 INDICATIONS AND USAGE

OZEMPIC is indicated:

- as an adjunct to diet and exercise to improve glycemic control in adults with type 2 diabetes mellitus.
- to reduce the risk of major adverse cardiovascular events (cardiovascular death, non-fatal myocardial infarction or non-fatal stroke) in adults with type 2 diabetes mellitus and established cardiovascular disease.
- to reduce the risk of sustained eGFR decline, end-stage kidney disease, and cardiovascular death in adults with type 2 diabetes mellitus and chronic kidney disease.

2 DOSAGE AND ADMINISTRATION

2.1 Important Administration Instructions

- Inspect OZEMPIC visually before use. It should appear clear and colorless. Do not use OZEMPIC if particulate matter and coloration is seen.
- Administer OZEMPIC once weekly, on the same day each week, at any time of the day, with or without meals.
- Inject OZEMPIC subcutaneously in the abdomen, thigh, or upper arm. Instruct patients to use a different injection site each week when injecting in the same body region.
- When using OZEMPIC with insulin, instruct patients to administer as separate injections and to never mix the products. It is acceptable to inject OZEMPIC and insulin in the same body region, but the injections should not be adjacent to each other.
- The day of weekly administration can be changed if necessary as long as the time between two doses is at least 2 days (>48 hours).
- If a dose is missed, administer OZEMPIC as soon as possible within 5 days after the missed dose. If more than 5 days have passed, skip the missed dose and administer the next dose on the regularly scheduled day. In each case, patients can then resume their regular once-weekly dosing schedule.

2.2 Recommended Dosage

Recommended Initiation Dosage

Initiate OZEMPIC with a dosage of 0.25 mg injected subcutaneously once weekly for 4 weeks. Follow the dosage escalation below to reduce the risk of gastrointestinal adverse reactions [see Warnings and Precautions (5.7), Adverse Reactions (6.1)].

After 4 weeks on the 0.25 mg dosage, increase the dosage to 0.5 mg once weekly.

Recommended Maintenance and Maximum Dosages for Glycemic Control

The recommended maintenance dosage is 0.5 mg, 1 mg, or 2 mg, injected subcutaneously once weekly, based on glycemic control.

If additional glycemic control is needed after at least 4 weeks on the:

- 0.5 mg dosage, the dosage may be increased to 1 mg once weekly.
- 1 mg dosage, the dosage may be increased to 2 mg once weekly.

The maximum recommended dosage is 2 mg once weekly.

Recommended Maintenance Dosage in Patients with Type 2 Diabetes Mellitus and Chronic Kidney Disease

Increase the dosage to the maintenance dosage, 1 mg once weekly, after at least 4 weeks on the 0.5 mg dosage.

3 DOSAGE FORMS AND STRENGTHS

Injection: clear, colorless solution available in 3 prefilled, disposable, single-patient-use pens:

Dose per Injection | Total Strength per Total Volume | Strength per mL
0.25 mg; 0.5 mg | 2 mg / 3 mL | 0.68 mg/mL
1 mg | 4 mg / 3 mL | 1.34 mg/mL
2 mg | 8 mg / 3 mL | 2.68 mg/mL

The 2 mg/1.5 mL (1.34 mg/mL) strength is not currently marketed by Novo Nordisk Inc.

4 CONTRAINDICATIONS

OZEMPIC is contraindicated in patients with:

- A personal or family history of MTC or in patients with MEN 2 [see Warnings and Precautions (5.1)].
- A serious hypersensitivity reaction to semaglutide or to any of the excipients in OZEMPIC. Serious hypersensitivity reactions including anaphylaxis and angioedema have been reported with OZEMPIC [see Warnings and Precautions (5.8)].

5 WARNINGS AND PRECAUTIONS

5.1 Risk of Thyroid C-Cell Tumors

In mice and rats, semaglutide caused a dose-dependent and treatment-duration-dependent increase in the incidence of thyroid C-cell tumors (adenomas and carcinomas) after lifetime exposure at clinically relevant plasma exposures [see Nonclinical Toxicology (13.1)]. It is unknown whether OZEMPIC causes thyroid C-cell tumors, including MTC, in humans as human relevance of semaglutide-induced rodent thyroid C-cell tumors has not been determined.

Cases of MTC in patients treated with liraglutide, another GLP-1 receptor agonist, have been reported in the postmarketing period; the data in these reports are insufficient to establish or exclude a causal relationship between MTC and GLP-1 receptor agonist use in humans.

OZEMPIC is contraindicated in patients with a personal or family history of MTC or in patients with MEN 2. Counsel patients regarding the potential risk for MTC with the use of OZEMPIC and inform them of symptoms of thyroid tumors (e.g., a mass in the neck, dysphagia, dyspnea, persistent hoarseness).

Routine monitoring of serum calcitonin or using thyroid ultrasound is of uncertain value for early detection of MTC in patients treated with OZEMPIC. Such monitoring may increase the risk of unnecessary procedures, due to the low-test specificity for serum calcitonin and a high background incidence of thyroid disease. Significantly elevated serum calcitonin value may indicate MTC and patients with MTC usually have calcitonin values >50 ng/L. If serum calcitonin is measured and found to be elevated, the patient should be further evaluated. Patients with thyroid nodules noted on physical examination or neck imaging should also be further evaluated.

5.2 Acute Pancreatitis

Acute pancreatitis, including fatal and non-fatal hemorrhagic or necrotizing pancreatitis, has been observed in patients treated with GLP-1 receptor agonists, including semaglutide [see Adverse Reactions (6.1)].

After initiation of OZEMPIC, observe patients carefully for signs and symptoms of acute pancreatitis which may include persistent or severe abdominal pain (sometimes radiating to the back) and which may or may not be accompanied by nausea or vomiting. If pancreatitis is suspected, discontinue OZEMPIC and initiate appropriate management.

5.3 Diabetic Retinopathy Complications

In a 2-year trial involving patients with type 2 diabetes and high cardiovascular risk, more events of diabetic retinopathy complications occurred in patients treated with OZEMPIC (3.0%) compared to placebo (1.8%). The absolute risk increase for diabetic retinopathy complications was larger among patients with a history of diabetic retinopathy at baseline (OZEMPIC 8.2%, placebo 5.2%) than among patients without a known history of diabetic retinopathy (OZEMPIC 0.7%, placebo 0.4%).

Rapid improvement in glucose control has been associated with a temporary worsening of diabetic retinopathy. The effect of long-term glycemic control with semaglutide on diabetic retinopathy complications has not been studied. Patients with a history of diabetic retinopathy should be monitored for progression of diabetic retinopathy.

5.4 Never Share an OZEMPIC Pen Between Patients

OZEMPIC pens must never be shared between patients, even if the needle is changed. Pen-sharing poses a risk for transmission of blood-borne pathogens.

5.5 Hypoglycemia with Concomitant Use of Insulin Secretagogues or Insulin

Patients receiving OZEMPIC in combination with an insulin secretagogue (e.g., sulfonylurea) or insulin may have an increased risk of hypoglycemia, including severe hypoglycemia [see Adverse Reactions (6.1), Drug Interactions (7)].

The risk of hypoglycemia may be lowered by a reduction in the dose of sulfonylurea (or other concomitantly administered insulin secretagogue) or insulin. Inform patients using these concomitant medications of the risk of hypoglycemia and educate them on the signs and symptoms of hypoglycemia.

5.6 Acute Kidney Injury Due to Volume Depletion

There have been postmarketing reports of acute kidney injury, in some cases requiring hemodialysis, in patients treated with semaglutide. The majority of the reported events occurred in patients who experienced gastrointestinal reactions leading to dehydration such as nausea, vomiting, or diarrhea [see Adverse Reactions (6.1)]. Monitor renal function in patients reporting adverse reactions to OZEMPIC that could lead to volume depletion, especially during dosage initiation and escalation of OZEMPIC.

5.7 Severe Gastrointestinal Adverse Reactions

Use of OZEMPIC has been associated with gastrointestinal adverse reactions, sometimes severe [see Adverse Reactions (6)]. In OZEMPIC clinical trials, severe gastrointestinal adverse reactions were reported more frequently among patients receiving OZEMPIC (0.5 mg 0.4%, 1 mg 0.8%) than placebo (0%). Severe gastrointestinal adverse reactions have also been reported postmarketing with GLP-1 receptor agonists.

OZEMPIC is not recommended in patients with severe gastroparesis.

5.8 Hypersensitivity Reactions

Serious hypersensitivity reactions (e.g., anaphylaxis, angioedema) have been reported in patients treated with OZEMPIC. If hypersensitivity reactions occur, discontinue use of OZEMPIC; treat promptly per standard of care, and monitor until signs and symptoms resolve. Do not use in patients with a previous hypersensitivity to OZEMPIC [see Contraindications (4), Adverse Reactions (6.2)].

Anaphylaxis and angioedema have been reported with other GLP-1 receptor agonists. Use caution in a patient with a history of angioedema or anaphylaxis with another GLP-1 receptor agonist because it is unknown whether such patients will be predisposed to anaphylaxis with OZEMPIC.

5.9 Acute Gallbladder Disease

Acute events of gallbladder disease such as cholelithiasis or cholecystitis have been reported in GLP-1 receptor agonist trials and postmarketing. In placebo-controlled trials, cholelithiasis was reported in 1.5% and 0.4% of patients-treated with OZEMPIC 0.5 mg and 1 mg, respectively. Cholelithiasis was not reported in placebo-treated patients. If cholelithiasis is suspected, gallbladder studies and appropriate clinical follow-up are indicated.

5.10 Pulmonary Aspiration During General Anesthesia or Deep Sedation

OZEMPIC delays gastric emptying [see Clinical Pharmacology (12.2)]. There have been rare postmarketing reports of pulmonary aspiration in patients receiving GLP-1 receptor agonists undergoing elective surgeries or procedures requiring general anesthesia or deep sedation who had residual gastric contents despite reported adherence to preoperative fasting recommendations.

Available data are insufficient to inform recommendations to mitigate the risk of pulmonary aspiration during general anesthesia or deep sedation in patients taking OZEMPIC, including whether modifying preoperative fasting recommendations or temporarily discontinuing OZEMPIC could reduce the incidence of retained gastric contents. Instruct patients to inform healthcare providers prior to any planned surgeries or procedures if they are taking OZEMPIC.

6 ADVERSE REACTIONS

The following serious adverse reactions are described below or elsewhere in the prescribing information:

- Risk of Thyroid C-cell Tumors [see Warnings and Precautions (5.1)]
- Acute Pancreatitis [see Warnings and Precautions (5.2)]
- Diabetic Retinopathy Complications [see Warnings and Precautions (5.3)]
- Hypoglycemia with Concomitant Use of Insulin Secretagogues or Insulin [see Warnings and Precautions (5.5)]
- Acute Kidney Injury Due to Volume Depletion [see Warnings and Precautions (5.6)]
- Severe Gastrointestinal Adverse Reactions [see Warnings and Precautions (5.7)]
- Hypersensitivity Reactions [see Warnings and Precautions (5.8)]
- Acute Gallbladder Disease [see Warnings and Precautions (5.9)]
- Pulmonary Aspiration During General Anesthesia or Deep Sedation [see Warnings and Precautions (5.10)]

6.1 Clinical Trials Experience

Because clinical trials are conducted under widely varying conditions, adverse reaction rates observed in the clinical trials of a drug cannot be directly compared to rates in the clinical trials of another drug and may not reflect the rates observed in practice.

Pool of Placebo-Controlled Trials

The data in Table 1 are derived from 2 placebo-controlled trials (1 monotherapy trial and 1 trial in combination with basal insulin) in patients with type 2 diabetes [see Clinical Studies (14)]. These data reflect exposure of 521 patients to OZEMPIC and a mean duration of exposure to OZEMPIC of 32.9 weeks. Across the treatment arms, the mean age of patients was 56 years, 3.4% were 75 years or older and 55% were male. In these trials 71% were White, 7% were Black or African American, and 19% were Asian; 21% identified as Hispanic or Latino ethnicity. At baseline, patients had type 2 diabetes for an average of 8.8 years and had a mean HbA1c of 8.2%. At baseline, 8.9% of the population reported retinopathy. Baseline estimated renal function was normal (eGFR ≥90 mL/min/1.73m^2) in 57.2%, mildly impaired (eGFR 60 to 90 mL/min/1.73m^2) in 35.9% and moderately impaired (eGFR 30 to 60 mL/min/1.73m^2) in 6.9% of patients.

Pool of Placebo- and Active-Controlled Trials

The occurrence of adverse reactions was also evaluated in a larger pool of patients with type 2 diabetes

participating in 7 placebo- and active-controlled glycemic control trials [see Clinical Studies (14)] including two trials in Japanese patients evaluating the use of OZEMPIC as monotherapy and add-on therapy to oral medications or insulin. In this pool, a total of 3150 patients with type 2 diabetes were treated with OZEMPIC for a mean duration of 44.9 weeks. Across the treatment arms, the mean age of patients was 57 years, 3.2% were 75 years or older and 57% were male. In these trials, 60% were White, 6% were Black or African American, and 31% were Asian; 16% identified as Hispanic or Latino ethnicity. At baseline, patients had type 2 diabetes for an average of 8.2 years and had a mean HbA1c of 8.2%. At baseline, 7.8% of the population reported retinopathy. Baseline estimated renal function was normal (eGFR ≥90 mL/min/1.73m^2) in 63.1%, mildly impaired (eGFR 60 to 90 mL/min/1.73m^2) in 34.3%, and moderately impaired (eGFR 30 to 60 mL/min/1.73m^2) in 2.5% of the patients.

Common Adverse Reactions

Table 1 shows common adverse reactions, excluding hypoglycemia, associated with the use of OZEMPIC in the pool of placebo-controlled trials. These adverse reactions occurred more commonly on OZEMPIC than on placebo and occurred in at least 5% of patients treated with OZEMPIC.

Table 1. Adverse Reactions in Placebo-Controlled Trials Reported in ≥5% of OZEMPIC-Treated Patients with Type 2 Diabetes Mellitus

Adverse Reaction | Placebo; (N=262); % | OZEMPIC 0.5 mg; (N=260); % | OZEMPIC 1 mg; (N=261); %
Nausea | 6.1 | 15.8 | 20.3
Vomiting | 2.3 | 5 | 9.2
Diarrhea | 1.9 | 8.5 | 8.8
Abdominal pain | 4.6 | 7.3 | 5.7
Constipation | 1.5 | 5 | 3.1

In the pool of placebo- and active-controlled trials and in the 2-year cardiovascular outcomes trial, the types and frequency of common adverse reactions, excluding hypoglycemia, were similar to those listed in Table 1.

In a clinical trial with 959 patients treated with OZEMPIC 1 mg or OZEMPIC 2 mg as add-on to metformin with or without sulfonylurea treatment for 40 weeks, no new safety signals were identified.

In the FLOW trial [see Clinical Studies (14.3)] in patients with type 2 diabetes mellitus and chronic kidney disease, safety data collection was limited to serious adverse events and selected predefined categories of adverse events regardless of seriousness. There were no new serious or severe adverse reactions identified in this trial.

Gastrointestinal Adverse Reactions

In the pool of placebo-controlled trials, gastrointestinal adverse reactions occurred more frequently among patients receiving OZEMPIC than placebo (placebo 15.3%, OZEMPIC 0.5 mg 32.7%, OZEMPIC 1 mg 36.4%). The majority of reports of nausea, vomiting, and/or diarrhea occurred during dose escalation. More patients receiving OZEMPIC 0.5 mg (3.1%) and OZEMPIC 1 mg (3.8%) discontinued treatment due to gastrointestinal adverse reactions than patients receiving placebo (0.4%).

In the trial with OZEMPIC 1 mg and 2 mg, gastrointestinal adverse reactions occurred more frequently among patients receiving OZEMPIC 2 mg (34%) vs OZEMPIC 1 mg (30.8%).

In addition to the reactions in Table 1, the following gastrointestinal adverse reactions with a frequency of <5% were associated with OZEMPIC (frequencies listed, respectively, as: placebo; 0.5 mg; 1 mg): dyspepsia (1.9%, 3.5%, 2.7%), eructation (0%, 2.7%, 1.1%), flatulence (0.8%, 0.4%, 1.5%), gastroesophageal reflux disease (0%, 1.9%, 1.5%), and gastritis (0.8%, 0.8%, 0.4%).

Other Adverse Reactions

Hypoglycemia

Table 2 summarizes the incidence of events related to hypoglycemia by various definitions in the placebo-controlled trials.

Table 2. Hypoglycemia Adverse Reactions in Placebo-Controlled Trials in Patients with Type 2 Diabetes Mellitus

 | Placebo | OZEMPIC 0.5 mg | OZEMPIC 1 mg
Monotherapy
(30 weeks) | N=129 | N=127 | N=130
Severe† | 0% | 0% | 0%
Documented symptomatic (≤70 mg/dL glucose threshold) | 0% | 1.6% | 3.8%
Severe† or Blood Glucose Confirmed Symptomatic (≤56 mg/dL glucose threshold) | 1.6% | 0% | 0%
Add-on to Basal Insulin with or without Metformin
(30 weeks) | N=132 | N=132 | N=131
Severe† | 0% | 0% | 1.5%
Documented symptomatic (≤70 mg/dL glucose threshold) | 15.2% | 16.7% | 29.8%
Severe† or Blood Glucose Confirmed Symptomatic (≤56 mg/dL glucose threshold) | 5.3% | 8.3% | 10.7%
† “Severe” hypoglycemia adverse reactions are episodes requiring the assistance of another person.

Hypoglycemia was more frequent when OZEMPIC was used in combination with a sulfonylurea [see Warnings and Precautions (5.5), Clinical Studies (14)]. Severe hypoglycemia occurred in 0.8% and 1.2% of patients when OZEMPIC 0.5 mg and 1 mg, respectively, was coadministered with a sulfonylurea. Documented symptomatic hypoglycemia occurred in 17.3% and 24.4% of patients when OZEMPIC 0.5 mg and 1 mg, respectively, was coadministered with a sulfonylurea. Severe or blood glucose confirmed symptomatic hypoglycemia occurred in 6.5% and 10.4% of patients when OZEMPIC 0.5 mg and 1 mg, respectively, was coadministered with a sulfonylurea.

Injection Site Reactions

In placebo-controlled trials, injection site reactions (e.g., injection-site discomfort, erythema) were reported in 0.2% of OZEMPIC-treated patients.

Increases in Amylase and Lipase

In placebo-controlled trials, patients exposed to OZEMPIC had a mean increase from baseline in amylase of 13% and lipase of 22%. These changes were not observed in placebo-treated patients.

Acute Pancreatitis

In glycemic control trials, acute pancreatitis was confirmed by adjudication in 7 OZEMPIC-treated patients (0.3 cases per 100 patient years) versus 3 in comparator-treated patients (0.2 cases per 100 patient years).

Cholelithiasis

In placebo-controlled trials, cholelithiasis was reported in 1.5% and 0.4% of patients-treated with OZEMPIC 0.5 mg and 1 mg, respectively. Cholelithiasis was not reported in placebo-treated patients.

Increases in Heart Rate

In placebo-controlled trials, OZEMPIC 0.5 mg and 1 mg resulted in a mean increase in heart rate of 2 to 3 beats per minute. There was a mean decrease in heart rate of 0.3 beats per minute in placebo-treated patients.

Fatigue, Dysgeusia and Dizziness

Other adverse reactions with a frequency of >0.4% were associated with OZEMPIC include fatigue, dysgeusia and dizziness.

6.2 Postmarketing Experience

The following adverse reactions have been reported during post-approval use of semaglutide, the active ingredient of OZEMPIC. Because these reactions are reported voluntarily from a population of uncertain size, it is not always possible to reliably estimate their frequency or establish a causal relationship to drug exposure.

Gastrointestinal: ileus, intestinal obstruction, severe constipation including fecal impaction

Hypersensitivity: anaphylaxis, angioedema, rash, urticaria

Hepatobiliary: cholecystitis, cholecystectomy

Neurologic: dysesthesia, headache

Pulmonary: Pulmonary aspiration has occurred in patients receiving GLP-1 receptor agonists undergoing elective surgeries or procedures requiring general anesthesia or deep sedation.

Renal: acute kidney injury

Skin and Subcutaneous Tissue: alopecia

7 DRUG INTERACTIONS

7.1 Concomitant Use with an Insulin Secretagogue (e.g., Sulfonylurea) or with Insulin

OZEMPIC stimulates insulin release in the presence of elevated blood glucose concentrations. Patients receiving OZEMPIC in combination with an insulin secretagogue (e.g., sulfonylurea) or insulin may have an increased risk of hypoglycemia, including severe hypoglycemia.

When initiating OZEMPIC, consider reducing the dose of concomitantly administered insulin secretagogue (such as sulfonylureas) or insulin to reduce the risk of hypoglycemia [see Warnings and Precautions (5.5), Adverse Reactions (6)].

7.2 Oral Medications

OZEMPIC causes a delay of gastric emptying, and thereby has the potential to impact the absorption of concomitantly administered oral medications. In clinical pharmacology trials, semaglutide did not affect the absorption of orally administered medications to any clinically relevant degree [see Clinical Pharmacology (12.3)]. Nonetheless, caution should be exercised when oral medications are concomitantly administered with OZEMPIC.

8 USE IN SPECIFIC POPULATIONS

8.1 Pregnancy

Risk Summary

There are limited data with semaglutide use in pregnant women to inform a drug-associated risk for adverse developmental outcomes. There are clinical considerations regarding the risks of poorly controlled diabetes in pregnancy (see Clinical Considerations). Based on animal reproduction studies, there may be potential risks to the fetus from exposure to semaglutide during pregnancy. OZEMPIC should be used during pregnancy only if the potential benefit justifies the potential risk to the fetus.

In pregnant rats administered semaglutide during organogenesis, embryofetal mortality, structural abnormalities and alterations to growth occurred at maternal clinical exposure based on AUC. In rabbits and cynomolgus monkeys administered semaglutide during organogenesis, early pregnancy losses or structural abnormalities were observed at clinical exposure (rabbit) and ≥2-fold the MRHD (monkey). These findings coincided with a marked maternal body weight loss in both animal species (see Data).

In the U.S. general population, the estimated background risk of major birth defects and miscarriage in clinically recognized pregnancies is 2 to 4% and 15 to 20%, respectively. The estimated background risk of major birth defects is 6 to 10% in women with pre-gestational diabetes with a peri-conceptional HbA1c >7 and has been reported to be as high as 20 to 25% in women with a peri-conceptional HbA1c >10. The estimated background risk of miscarriage for the indicated population is unknown.

Clinical Considerations

Disease-Associated Maternal and/or Embryo/fetal Risk

Hypoglycemia and hyperglycemia occur more frequently during pregnancy in patients with pre-gestational diabetes. Poorly controlled diabetes during pregnancy increases the maternal risk for diabetic ketoacidosis, pre- eclampsia, spontaneous abortions, preterm delivery, and delivery complications. Poorly controlled diabetes increases the fetal risk for major birth defects, stillbirth, and macrosomia related morbidity.

Data

Animal Data

In a combined fertility and embryofetal development study in rats, subcutaneous doses of 0.01, 0.03 and 0.09 mg/kg/day (0.06-, 0.2-, and 0.6-fold the MRHD) were administered to males for 4 weeks prior to and throughout mating and to females for 2 weeks prior to mating, and throughout organogenesis to Gestation Day 17. In parental animals, pharmacologically mediated reductions in body weight gain and food consumption were observed at all dose levels. In the offspring, reduced growth and fetuses with visceral (heart blood vessels) and skeletal (cranial bones, vertebra, ribs) abnormalities were observed at the human exposure.

In an embryofetal development study in pregnant rabbits, subcutaneous doses of 0.0010, 0.0025 or 0.0075 mg/kg/day (0.02-, 0.2-, and 1.2-fold the MRHD) were administered throughout organogenesis from Gestation Day 6 to 19. Pharmacologically mediated reductions in maternal body weight gain and food consumption were observed at all dose levels. Early pregnancy losses and increased incidences of minor visceral (kidney, liver) and skeletal (sternebra) fetal abnormalities were observed at ≥0.0025 mg/kg/day, at clinically relevant exposures.

In an embryofetal development study in pregnant cynomolgus monkeys, subcutaneous doses of 0.015, 0.075, and 0.15 mg/kg twice weekly (0.5-, 3-, and 8-fold the MRHD) were administered throughout organogenesis, from Gestation Day 16 to 50. Pharmacologically mediated, marked initial maternal body weight loss and reductions in body weight gain and food consumption coincided with the occurrence of sporadic abnormalities (vertebra, sternebra, ribs) at ≥0.075 mg/kg twice weekly (≥3X human exposure).

In a pre- and postnatal development study in pregnant cynomolgus monkeys, subcutaneous doses of 0.015, 0.075, and 0.15 mg/kg twice weekly (0.3-, 2-, and 4-fold the MRHD) were administered from Gestation Day 16 to 140. Pharmacologically mediated marked initial maternal body weight loss and reductions in body weight gain and food consumption coincided with an increase in early pregnancy losses and led to delivery of slightly smaller offspring at ≥0.075 mg/kg twice weekly (≥2X human exposure).

8.2 Lactation

Risk Summary

There are no data on the presence of semaglutide in human milk, the effects on the breastfed infant, or the effects on milk production. Semaglutide was present in the milk of lactating rats, however, due to species-specific differences in lactation physiology, the clinical relevance of these data are not clear (see Data). The developmental and health benefits of breastfeeding should be considered along with the mother’s clinical need for OZEMPIC and any potential adverse effects on the breastfed infant from OZEMPIC or from the underlying maternal condition.

Data

In lactating rats, semaglutide was detected in milk at levels 3- to 12- fold lower than in maternal plasma.

8.3 Females and Males of Reproductive Potential

Discontinue OZEMPIC in women at least 2 months before a planned pregnancy due to the long washout period for semaglutide [see Use in Specific Populations (8.1)].

8.4 Pediatric Use

Safety and efficacy of OZEMPIC have not been established in pediatric patients.

8.5 Geriatric Use

In the pool of placebo- and active-controlled glycemic control trials, 744 (23.6%) OZEMPIC-treated patients were 65 years of age and over and 102 OZEMPIC-treated patients (3.2%) patients were 75 years of age and over. In SUSTAIN 6, the cardiovascular outcome trial, 788 (48%) OZEMPIC-treated patients were 65 years of age and over and 157 OZEMPIC-treated patients (9.6%) patients were 75 years of age and over.

No overall differences in safety or efficacy were detected between these patients and younger patients, but greater sensitivity of some older individuals cannot be ruled out.

8.6 Renal Impairment

No dose adjustment of OZEMPIC is recommended for patients with renal impairment. In subjects with renal impairment including kidney failure, no clinically relevant change in semaglutide pharmacokinetics (PK) was observed [see Clinical Pharmacology (12.3)].

8.7 Hepatic Impairment

No dose adjustment of OZEMPIC is recommended for patients with hepatic impairment. In a study in subjects with different degrees of hepatic impairment, no clinically relevant change in semaglutide pharmacokinetics (PK) was observed [see Clinical Pharmacology (12.3)].

10 OVERDOSAGE

In the event of overdose, appropriate supportive treatment should be initiated according to the patient’s clinical signs and symptoms. Consider contacting the Poison Help line (1-800-222-1222) or a medical toxicologist for additional overdosage management recommendations. A prolonged period of observation and treatment for these symptoms may be necessary, taking into account the long half-life of OZEMPIC of approximately 1 week.

11 DESCRIPTION

OZEMPIC (semaglutide) injection, for subcutaneous use, contains semaglutide, a human GLP-1 receptor agonist (or GLP-1 analog). The peptide backbone is produced by yeast fermentation. The main protraction mechanism of semaglutide is albumin binding, facilitated by modification of position 26 lysine with a hydrophilic spacer and a C18 fatty di-acid. Furthermore, semaglutide is modified in position 8 to provide stabilization against degradation by the enzyme dipeptidyl-peptidase 4 (DPP-4). A minor modification was made in position 34 to ensure the attachment of only one fatty di-acid. The molecular formula is C187H291N45O59 and the molecular weight is 4113.58 g/mol.

Structural formula:

OZEMPIC is a sterile, aqueous, clear, colorless solution. Each 3 mL prefilled single-patient-use pen contains semaglutide 2 mg (0.68 mg/mL), 4 mg (1.34 mg/mL), or 8 mg (2.68 mg/mL). Each 1 mL of OZEMPIC solution also contains the following inactive ingredients: disodium phosphate dihydrate, 1.42 mg; propylene glycol, 14 mg; phenol, 5.5 mg; and water for injections. OZEMPIC has a pH of approximately 7.4. Hydrochloric acid or sodium hydroxide may be added to adjust pH. The 2 mg/1.5 mL (1.34 mg/mL) strength is not currently marketed by Novo Nordisk Inc.

12 CLINICAL PHARMACOLOGY

12.1 Mechanism of Action

Semaglutide is a GLP-1 analogue with 94% sequence homology to human GLP-1. Semaglutide acts as a GLP-1 receptor agonist that selectively binds to and activates the GLP-1 receptor, the target for native GLP-1.

GLP-1 is a physiological hormone that has multiple actions on glucose, mediated by the GLP-1 receptors.

The principal mechanism of protraction resulting in the long half-life of semaglutide is albumin binding, which results in decreased renal clearance and protection from metabolic degradation. Furthermore, semaglutide is stabilized against degradation by the DPP-4 enzyme.

Semaglutide reduces blood glucose through a mechanism where it stimulates insulin secretion and lowers glucagon secretion, both in a glucose-dependent manner. Thus, when blood glucose is high, insulin secretion is stimulated, and glucagon secretion is inhibited. The mechanism of blood glucose lowering also involves a minor delay in gastric emptying in the early postprandial phase.

The mechanism of kidney-related risk reduction has not been established.

12.2 Pharmacodynamics

Semaglutide lowers fasting and postprandial blood glucose and reduces body weight. All pharmacodynamic evaluations were performed after 12 weeks of treatment (including dose escalation) at steady state with semaglutide 1 mg.

Fasting and Postprandial Glucose

Semaglutide reduces fasting and postprandial glucose concentrations. In patients with type 2 diabetes, treatment with semaglutide 1 mg resulted in reductions in glucose in terms of absolute change from baseline and relative reduction compared to placebo of 29 mg/dL (22%) for fasting glucose, 74 mg/dL (36%) for 2-hour postprandial glucose, and 30 mg/dL (22%) for mean 24-hour glucose concentration (see Figure 1).

Figure 1. Mean 24-hour Plasma Glucose Profiles (standardized meals) in Patients with Type 2 Diabetes before (Baseline) and after 12 Weeks of Treatment with Semaglutide or Placebo

Insulin Secretion

Both first-and second-phase insulin secretion are increased in patients with type 2 diabetes treated with OZEMPIC compared with placebo.

Glucagon Secretion

Semaglutide lowers the fasting and postprandial glucagon concentrations. In patients with type 2 diabetes, treatment with semaglutide resulted in the following relative reductions in glucagon compared to placebo, fasting glucagon (8%), postprandial glucagon response (14 to 15%), and mean 24-hour glucagon concentration (12%).

Glucose dependent insulin and glucagon secretion

Semaglutide lowers high blood glucose concentrations by stimulating insulin secretion and lowering glucagon secretion in a glucose-dependent manner. With semaglutide, the insulin secretion rate in patients with type 2 diabetes was similar to that of healthy subjects (see Figure 2).

Figure 2. Mean Insulin Secretion Rate Versus Glucose Concentration in Patients with Type 2 Diabetes during Graded Glucose Infusion before (Baseline) and after 12 Weeks of Treatment with Semaglutide or Placebo and in Untreated Healthy Subjects

During induced hypoglycemia, semaglutide did not alter the counter regulatory responses of increased glucagon compared to placebo and did not impair the decrease of C-peptide in patients with type 2 diabetes.

Gastric emptying

Semaglutide causes a delay of early postprandial gastric emptying, thereby reducing the rate at which glucose appears in the circulation postprandially.

Cardiac electrophysiology (QTc)

The effect of semaglutide on cardiac repolarization was tested in a thorough QTc trial. Semaglutide does not prolong QTc intervals at doses up to 1.5 mg at steady-state.

12.3 Pharmacokinetics

Absorption

Absolute bioavailability of semaglutide is 89%. Maximum concentration of semaglutide is reached 1 to 3 days post dose.

Similar exposure is achieved with subcutaneous administration of semaglutide in the abdomen, thigh, or upper arm.

In patients with type 2 diabetes, semaglutide exposure increases in a dose-proportional manner for once-weekly doses of 0.5 mg, 1 mg and 2 mg. Steady-state exposure is achieved following 4 to 5 weeks of once-weekly administration. In patients with type 2 diabetes, the mean population-PK estimated steady-state concentrations following once-weekly subcutaneous administration of 0.5 mg and 1 mg semaglutide were approximately 65 ng/mL and 123 ng/mL, respectively. In the trial comparing semaglutide 1 mg and 2 mg, the mean steady state concentrations were 111.1 ng/mL and 222.1 ng/mL, respectively.

Distribution

The mean apparent volume of distribution of semaglutide following subcutaneous administration in patients with type 2 diabetes is approximately 12.5L. Semaglutide is extensively bound to plasma albumin (>99%).

Elimination

The apparent clearance of semaglutide in patients with type 2 diabetes is approximately 0.05 L/h. With an elimination half-life of approximately 1 week, semaglutide will be present in the circulation for about 5 weeks after the last dose.

Metabolism

The primary route of elimination for semaglutide is metabolism following proteolytic cleavage of the peptide backbone and sequential beta-oxidation of the fatty acid sidechain.

Excretion

The primary excretion routes of semaglutide-related material are via the urine and feces. Approximately 3% of the dose is excreted in the urine as intact semaglutide.

Specific Populations

Based on a population pharmacokinetic analysis, age, sex, race, and ethnicity, and renal impairment do not have a clinically meaningful effect on the pharmacokinetics of semaglutide. The exposure of semaglutide decreases with an increase in body weight. However, semaglutide doses of 0.5 mg and 1 mg provide adequate systemic exposure over the body weight range of 40 to 198 kg evaluated in the clinical trials. The effects of intrinsic factors on the pharmacokinetics of semaglutide are shown in Figure 3.

Figure 3. Impact of Intrinsic Factors on Semaglutide Exposure

Patients with Renal impairment - Renal impairment does not impact the pharmacokinetics of semaglutide in a clinically relevant manner. This was shown in a study with a single dose of 0.5 mg semaglutide in patients with different degrees of renal impairment (mild, moderate, severe, or kidney failure) compared with subjects with normal renal function. This was also shown for subjects with both type 2 diabetes and renal impairment based on data from clinical studies (Figure 3).

Patients with Hepatic impairment - Hepatic impairment does not have any impact on the exposure of semaglutide. The pharmacokinetics of semaglutide were evaluated in patients with different degrees of hepatic impairment (mild, moderate, severe) compared with subjects with normal hepatic function in a study with a single-dose of 0.5 mg semaglutide.

Pediatric Patients- Semaglutide has not been studied in pediatric patients.

Drug Interaction Studies

In vitro studies have shown very low potential for semaglutide to inhibit or induce CYP enzymes, and to inhibit drug transporters.

The delay of gastric emptying with semaglutide may influence the absorption of concomitantly administered oral medicinal products [see Drug Interactions (7.2)]. The potential effect of semaglutide on the absorption of co-administered oral medications was studied in trials at semaglutide 1 mg steady-state exposure.

No clinically relevant drug-drug interaction with semaglutide (Figure 4) was observed based on the evaluated medications; therefore, no dose adjustment is required when co-administered with semaglutide. In a separate study, no apparent effect on the rate of gastric emptying was observed with semaglutide 2.4 mg.

Figure 4. Impact of Semaglutide on the Exposure of Coadministered Oral Medications

Relative exposure in terms of AUC and Cmax for each medication when given with semaglutide compared to without semaglutide. Metformin and oral contraceptive drug (ethinylestradiol/levonorgestrel) were assessed at steady state. Warfarin (S-warfarin/R-warfarin), digoxin and atorvastatin were assessed after a single dose.

Abbreviations: AUC: area under the curve. Cmax: maximum concentration. CI: confidence interval.

12.6 Immunogenicity

The observed incidence of anti-drug antibodies is highly dependent on the sensitivity and specificity of the assay. Differences in assay methods preclude meaningful comparisons of the incidence of anti-drug antibodies (ADAs) in the studies described below with the incidence of ADAs in other studies, including those of semaglutide or of other semaglutide products.

Across the placebo- and active-controlled glycemic control trials, 32 out of 3,150 (1%) OZEMPIC-treated patients developed ADAs to the active ingredient in OZEMPIC (i.e., semaglutide). Of the 32 semaglutide- treated patients that developed semaglutide ADAs, 19 patients (0.6% of the overall population) developed antibodies cross-reacting with native GLP-1. The in vitro neutralizing activity of the antibodies is uncertain at this time.

13 NONCLINICAL TOXICOLOGY

13.1 Carcinogenesis, Mutagenesis, Impairment of Fertility

In a 2-year carcinogenicity study in CD-1 mice, subcutaneous doses of 0.3, 1 and 3 mg/kg/day [2-, 11-, and 30-fold the maximum recommended human dose (MRHD) of 2 mg/week, based on AUC] were administered to the males, and 0.1, 0.3 and 1 mg/kg/day (1-, 2-, and 7-fold MRHD) were administered to the females. A statistically significant increase in thyroid C-cell adenomas and a numerical increase in C-cell carcinomas were observed in males and females at clinically relevant exposures.

In a 2-year carcinogenicity study in Sprague Dawley rats, subcutaneous doses of 0.0025, 0.01, 0.025 and 0.1 mg/kg/day were administered (below quantification, 0.2-, 0.5-, and 3-fold the exposure at the MRHD). A statistically significant increase in thyroid C-cell adenomas was observed in males and females at all dose levels, and a statistically significant increase in thyroid C-cell carcinomas was observed in males at ≥0.01 mg/kg/day, at clinically relevant exposures.

Human relevance of thyroid C-cell tumors in rats is unknown and could not be determined by clinical studies or nonclinical studies [see Boxed Warning, Warnings and Precautions (5.1)].

Semaglutide was not mutagenic or clastogenic in a standard battery of genotoxicity tests (bacterial mutagenicity (Ames), human lymphocyte chromosome aberration, rat bone marrow micronucleus).

In a combined fertility and embryo-fetal development study in rats, subcutaneous doses of 0.01, 0.03 and 0.09 mg/kg/day (0.06-, 0.2-, and 0.6-fold the MRHD) were administered to male and female rats. Males were dosed for 4 weeks prior to mating, and females were dosed for 2 weeks prior to mating and throughout organogenesis until Gestation Day 17. No effects were observed on male fertility. In females, an increase in estrus cycle length was observed at all dose levels, together with a small reduction in numbers of corpora lutea at ≥0.03 mg/kg/day. These effects were likely an adaptive response secondary to the pharmacological effect of semaglutide on food consumption and body weight.

14 CLINICAL STUDIES

14.1 Glycemic Control Trials in Adults with Type 2 Diabetes Mellitus

OZEMPIC has been studied as monotherapy and in combination with metformin, metformin and sulfonylureas, metformin and/or thiazolidinedione, and basal insulin in patients with type 2 diabetes mellitus. The efficacy of OZEMPIC was compared with placebo, sitagliptin, exenatide extended-release (ER), and insulin glargine.

Most trials evaluated the use of OZEMPIC 0.5 mg, and 1 mg, with the exception of the trial comparing OZEMPIC and exenatide ER where only the 1 mg dose was studied. One trial evaluated the use of OZEMPIC 2 mg once weekly.

In patients with type 2 diabetes mellitus, OZEMPIC produced clinically relevant reduction from baseline in HbA1c compared with placebo.

The efficacy of OZEMPIC was not impacted by age, gender, race, ethnicity, BMI at baseline, body weight (kg) at baseline, diabetes duration and level of renal function impairment.

Monotherapy Use of OZEMPIC in Adults with Type 2 Diabetes Mellitus

In a 30-week double-blind trial (NCT02054897), 388 patients with type 2 diabetes mellitus inadequately controlled with diet and exercise were randomized to OZEMPIC 0.5 mg or OZEMPIC 1 mg once weekly or placebo. Patients had a mean age of 54 years and 54% were men. The mean duration of type 2 diabetes was 4.2 years, and the mean BMI was 33 kg/m^2. Overall, 64% were White, 8% were Black or African American, and 21% were Asian; 30% identified as Hispanic or Latino ethnicity.

Monotherapy with OZEMPIC 0.5 mg and 1 mg once weekly for 30 weeks resulted in a statistically significant reduction in HbA1c compared with placebo (see Table 3).

Table 3. Results at Week 30 in a Trial of OZEMPIC as Monotherapy in Adult Patients with Type 2 Diabetes Mellitus Inadequately Controlled with Diet and Exercise

 | Placebo | OZEMPIC 0.5 mg | OZEMPIC 1 mg
Intent-to-Treat (ITT) Population (N)a | 129 | 128 | 130
HbA1c (%)
Baseline (mean) | 8 | 8.1 | 8.1
Change at week 30b | -0.1 | -1.4 | -1.6
Difference from placebob [95% CI] |  | -1.2 [-1.5, -0.9]c | -1.4 [-1.7, -1.1]c
Patients (%) achieving HbA1c <7% | 28 | 73 | 70
FPG (mg/dL)
Baseline (mean) | 174 | 174 | 179
Change at week 30b | -15 | -41 | -44

a The intent-to-treat population includes all randomized and exposed patients. At week 30 the primary HbA1c endpoint was missing for 10%, 7% and 7% of patients and during the trial rescue medication was initiated by 20%, 5% and 4% of patients randomized to placebo, OZEMPIC 0.5 mg and OZEMPIC 1 mg, respectively. Missing data were imputed using multiple imputation based on retrieved dropouts.
b Intent-to-treat analysis using ANCOVA adjusted for baseline value and country.
c p<0.0001 (2-sided) for superiority, adjusted for multiplicity.

The mean baseline body weight was 89.1 kg, 89.8 kg, 96.9 kg in the placebo, OZEMPIC 0.5 mg, and OZEMPIC 1 mg arms, respectively. The mean changes from baseline to week 30 were -1.2 kg, -3.8 kg and -4.7 kg in the placebo, OZEMPIC 0.5 mg, and OZEMPIC 1 mg arms, respectively. The difference from placebo (95% CI) for OZEMPIC 0.5 mg was -2.6 kg (-3.8, -1.5), and for OZEMPIC 1 mg was -3.5 kg (-4.8, -2.2).

Combination Therapy Use of OZEMPIC in Adults with Type 2 Diabetes Mellitus

Combination with metformin and/or thiazolidinediones

In a 56-week, double-blind trial (NCT01930188), 1231 patients with type 2 diabetes mellitus were randomized to OZEMPIC 0.5 mg once weekly, OZEMPIC 1 mg once weekly, or sitagliptin 100 mg once daily, all in combination with metformin (94%) and/or thiazolidinediones (6%). Patients had a mean age of 55 years and 51% were men. The mean duration of type 2 diabetes was 6.6 years, and the mean BMI was 32 kg/m^2. Overall, 68% were White, 5% were Black or African American, and 25% were Asian; 17% identified as Hispanic or Latino ethnicity.

Treatment with OZEMPIC 0.5 mg and 1 mg once weekly for 56 weeks resulted in a statistically significant reduction in HbA1c compared to sitagliptin (see Table 4 and Figure 5).

Table 4. Results at Week 56 in a Trial of OZEMPIC Compared to Sitagliptin in Adult Patients with Type 2 Diabetes Mellitus in Combination with Metformin and/or Thiazolidinediones

 | OZEMPIC; 0.5 mg | OZEMPIC; 1 mg | Sitagliptin
Intent-to-Treat (ITT) Population (N)a | 409 | 409 | 407
HbA1c (%)
Baseline (mean) | 8 | 8 | 8.2
Change at week 56b | -1.3 | -1.5 | -0.7
Difference from sitagliptinb [95% CI] | -0.6; [-0.7, -0.4]c | -0.8; [-0.9, -0.6]c
Patients (%) achieving HbA1c <7% | 66 | 73 | 40
FPG (mg/dL)
Baseline (mean) | 168 | 167 | 173
Change at week 56b | -35 | -43 | -23

a The intent-to-treat population includes all randomized and exposed patients. At week 56 the primary HbA1c endpoint was missing for 7%, 5% and 6% of patients and during the trial rescue medication was initiated by 5%, 2% and 19% of patients randomized to OZEMPIC 0.5 mg, OZEMPIC 1 mg and sitagliptin, respectively. Missing data were imputed using multiple imputation based on retrieved dropouts.
b Intent-to-treat analysis using ANCOVA adjusted for baseline value and country.
c p<0.0001 (2-sided) for superiority, adjusted for multiplicity.

The mean baseline body weight was 89.9 kg, 89.2 kg, 89.3 kg in the OZEMPIC 0.5 mg, OZEMPIC 1 mg, and sitagliptin arms, respectively. The mean changes from baseline to week 56 were -4.2 kg, -5.5 kg, and -1.7 kg for the OZEMPIC 0.5 mg, OZEMPIC 1 mg, and sitagliptin arms, respectively. The difference from sitagliptin (95% CI) for OZEMPIC 0.5 mg was -2.5 kg (-3.2, -1.8), and for OZEMPIC 1 mg was -3.8 kg (-4.5, -3.1).

Figure 5. Mean HbA1c (%) Over Time - Baseline to Week 56

Combination with metformin or metformin with sulfonylurea

In a 56-week, open-label trial (NCT01885208), 813 patients with type 2 diabetes mellitus on metformin alone (49%), metformin with sulfonylurea (45%), or other (6%) were randomized to OZEMPIC 1 mg once weekly or exenatide 2 mg once weekly. Patients had a mean age of 57 years and 55% were men. The mean duration of type 2 diabetes was 9 years, and the mean BMI was 34 kg/m^2. Overall, 84% were White, 7% were Black or African American, and 2% were Asian; 24% identified as Hispanic or Latino ethnicity.

Treatment with OZEMPIC 1 mg once weekly for 56 weeks resulted in a statistically significant reduction in HbA1c compared to exenatide 2 mg once weekly (see Table 5).

Table 5. Results at Week 56 in a Trial of OZEMPIC Compared to Exenatide 2 mg Once Weekly in Adult Patients with Type 2 Diabetes Mellitus in Combination with Metformin or Metformin with Sulfonylurea

 | OZEMPIC 1 mg | Exenatide ER 2 mg
Intent-to-Treat (ITT) Population (N)a | 404 | 405
HbA1c (%)
Baseline (mean) | 8.4 | 8.3
Change at week 56b | -1.4 | -0.9
Difference from exenatideb [95% CI] | -0.5; [-0.7, -0.3]c
Patients (%) achieving HbA1c <7% | 62 | 40
FPG (mg/dL)
Baseline (mean) | 191 | 188
Change at week 56b | -44 | -34

a The intent-to-treat population includes all randomized and exposed patients. At week 56 the primary HbA1c endpoint was missing for 9% and 11% of patients and during the trial rescue medication was initiated by 5% and 10% of patients randomized to OZEMPIC 1 mg and exenatide ER 2 mg, respectively. Missing data were imputed using multiple imputation based on retrieved dropouts.
b Intent-to-treat analysis using ANCOVA adjusted for baseline value and country.
c p<0.0001 (2-sided) for superiority, adjusted for multiplicity.

The mean baseline body weight was 96.2 kg and 95.4 kg in the OZEMPIC 1 mg and exenatide ER arms, respectively. The mean changes from baseline to week 56 were -4.8 kg and -2 kg in the OZEMPIC 1 mg and exenatide ER arms, respectively. The difference from exenatide ER (95% CI) for OZEMPIC 1 mg was -2.9 kg (-3.6, -2.1).

Combination with metformin or metformin with sulfonylurea

In a 30-week, open-label trial (NCT02128932), 1089 patients with type 2 diabetes mellitus were randomized to OZEMPIC 0.5 mg once weekly, OZEMPIC 1 mg once weekly, or insulin glargine once daily on a background of metformin (48%) or metformin and sulfonylurea (51%). Patients had a mean age of 57 years and 53% were men. The mean duration of type 2 diabetes was 8.6 years, and the mean BMI was 33 kg/m^2. Overall, 77% were White, 9% were Black or African American, and 11% were Asian; 20% identified as Hispanic or Latino ethnicity.

Patients assigned to insulin glargine had a baseline mean HbA1c of 8.1% and were started on a dose of 10 U once daily. Insulin glargine dose adjustments occurred throughout the trial period based on self-measured fasting plasma glucose before breakfast, targeting 71 to <100 mg/dL. In addition, investigators could titrate insulin glargine at their discretion between study visits. Only 26% of patients had been titrated to goal by the primary endpoint at week 30, at which time the mean daily insulin dose was 29 U per day.

Treatment with OZEMPIC 0.5 mg and 1 mg once weekly for 30 weeks resulted in a statistically significant reduction in HbA1c compared with the insulin glargine titration implemented in this study protocol (see Table 6).

Table 6. Results at Week 30 in a Trial of OZEMPIC Compared to Insulin Glargine in Adult Patients with Type 2 Diabetes Mellitus in Combination with Metformin or Metformin with Sulfonylurea

 | OZEMPIC 0.5 mg | OZEMPIC 1 mg | Insulin Glargine
Intent-to-Treat (ITT) Population (N)a | 362 | 360 | 360
HbA1c (%)
Baseline (mean) | 8.1 | 8.2 | 8.1
Change at week 30b | -1.2 | -1.5 | -0.9
Difference from insulin glargineb [95% CI] | -0.3 [-0.5, -0.1]c | -0.6 [-0.8, -0.4]c
Patients (%) achieving HbA1c <7% | 55 | 66 | 40
FPG (mg/dL)
Baseline (mean) | 172 | 179 | 174
Change at week 30b | -35 | -46 | -37

a The intent-to-treat population includes all randomized and exposed patients. At week 30 the primary HbA1c endpoint was missing for 8%, 6% and 6% of patients and during the trial rescue medication was initiated by 4%, 3% and 1% of patients randomized to OZEMPIC 0.5 mg, OZEMPIC 1 mg and insulin glargine, respectively. Missing data were imputed using multiple imputation based on retrieved dropouts.
b Intent-to-treat analysis using ANCOVA adjusted for baseline value, country and stratification factors.
c p<0.0001 (2-sided) for superiority, adjusted for multiplicity.
The mean baseline body weight was 93.7 kg, 94 kg, 92.6 kg in the OZEMPIC 0.5 mg, OZEMPIC 1 mg, and insulin glargine arms, respectively. The mean changes from baseline to week 30 were -3.2 kg, -4.7 kg and 0.9 kg in the OZEMPIC 0.5 mg, OZEMPIC 1 mg, and insulin glargine arms, respectively. The difference from insulin glargine (95% CI) for OZEMPIC 0.5 mg was -4.1 kg (-4.9, -3.3) and for OZEMPIC 1 mg was -5.6 kg (-6.4, -4.8).
Combination with metformin or metformin with sulfonylurea
In a 40-week, double-blind trial (NCT03989232), 961 patients with type 2 diabetes currently treated with metformin with or without sulfonylurea treatment were randomized to OZEMPIC 2 mg or OZEMPIC 1 mg once weekly. Patients had a mean age of 58 years and 58.6% were men. The mean duration of type 2 diabetes was 9.5 years and the mean BMI was 34.6 kg/m^2. At randomization, 53.3% of patients were treated with sulfonylurea and metformin. Overall, 88.1% were White, 4.5% were Black or African American, and 7.2% were Asian; 11.6% identified as Hispanic or Latino ethnicity. Treatment with OZEMPIC 2 mg once weekly for 40 weeks resulted in a statistically significant reduction in HbA1c compared with OZEMPIC 1 mg (see Table 7). Patients were stratified by region (Japan/outside Japan) at randomization.

Table 7. Results at Week 40 in a Trial of OZEMPIC 2 mg Compared to OZEMPIC 1 mg in Adult Patients with Type 2 Diabetes Mellitus in Combination With Metformin or Metformin with Sulfonylurea

 | OZEMPIC 1 mg | OZEMPIC 2 mg
Intent-to-Treat (ITT) Population (N)a | 481 | 480
HbA1c (%)
Baseline (mean) | 8.8 | 8.9
Change at week 40b | -1.9 | -2.1
Difference from OZEMPIC 1 mg [95% CI] |  | -0.2 [-0.31 ; -0.04]c
Patients (%) achieving HbA1c <7%a | 56 | 64
FPG (mg/dL)
Baseline (mean) | 196 | 193
Change at week 40b | -55 | -59

aThe intent-to-treat population includes all randomized subjects. At week 40 the primary HbA1c endpoint was missing for 3% and 5% of patients randomized to OZEMPIC 1 mg and OZEMPIC 2 mg, respectively. Missing data were imputed using multiple imputation based on retrieved dropouts. For calculation of proportions, imputed values are dichotomized and the denominator is the number of all randomized subjects.
b Intent-to-treat analysis using ANCOVA adjusted for baseline value and stratification factor.
c p<0.01 (2-sided) for superiority, adjusted for multiplicity.

The mean baseline body weight was 98.6 kg and 100.1 kg in the OZEMPIC 1 mg and OZEMPIC 2 mg arms, respectively. The mean changes from baseline to week 40 were -5.6 kg and -6.4 kg in the OZEMPIC 1 mg and OZEMPIC 2 mg arms, respectively. The difference between treatment arms in body weight change from baseline at week 40 was not statistically significant.

Combination with basal insulin

In a 30-week, double-blind trial (NCT02305381), 397 patients with type 2 diabetes mellitus inadequately controlled with basal insulin, with or without metformin, were randomized to OZEMPIC 0.5 mg once weekly, OZEMPIC 1 mg once weekly, or placebo. Patients with HbA1c ≤8.0% at screening reduced their insulin dose by 20% at start of the trial to reduce the risk of hypoglycemia. Patients had a mean age of 59 years and 56% were men. The mean duration of type 2 diabetes was 13 years, and the mean BMI was 32 kg/m^2. Overall, 78% were White, 5% were Black or African American, and 17% were Asian; 12% identified as Hispanic or Latino ethnicity.

Treatment with OZEMPIC resulted in a statistically significant reduction in HbA1c after 30 weeks of treatment compared to placebo (see Table 8).

Table 8. Results at Week 30 in a Trial of OZEMPIC in Adult Patients with Type 2 Diabetes Mellitus in Combination with Basal Insulin with or without Metformin

 | Placebo | OZEMPIC 0.5 mg | OZEMPIC 1 mg
Intent-to-Treat (ITT) Population (N)a | 133 | 132 | 131
HbA1c (%)
Baseline (mean) | 8.4 | 8.4 | 8.3
Change at week 30b | -0.2 | -1.3 | -1.7
Difference from placebob [95% CI] |  | -1.1 [-1.4, -0.8]c | -1.6 [-1.8, -1.3]c
Patients (%) achieving HbA1c <7% | 13 | 56 | 73
FPG (mg/dL)
Baseline (mean) | 154 | 161 | 153
Change at week 30b | -8 | -28 | -39

a The intent-to-treat population includes all randomized and exposed patients. At week 30 the primary HbA1c endpoint was missing for 7%, 5% and 5% of patients and during the trial rescue medication was initiated by 14%, 2% and 1% of patients randomized to placebo, OZEMPIC 0.5 mg and OZEMPIC 1 mg, respectively. Missing data were imputed using multiple imputation based on retrieved dropouts.
b Intent-to-treat analysis using ANCOVA adjusted for baseline value, country and stratification factors.
c p<0.0001 (2-sided) for superiority, adjusted for multiplicity.

The mean baseline body weight was 89.9 kg, 92.7 kg, and 92.5 kg in the placebo, OZEMPIC 0.5 mg, and OZEMPIC 1 mg arms, respectively. The mean changes from baseline to week 30 were -1.2 kg, -3.5 kg, and -6 kg in the placebo, OZEMPIC 0.5 mg, and OZEMPIC 1 mg arms, respectively. The difference from placebo (95% CI) for OZEMPIC 0.5 mg was -2.2 kg (-3.4, -1.1), and for OZEMPIC 1 mg was -4.7 kg (-5.8, -3.6).

14.2 Cardiovascular Outcomes Trial of OZEMPIC in Adults with Type 2 Diabetes Mellitus and Cardiovascular Disease

SUSTAIN 6 (NCT01720446) was a multi-center, multi-national, placebo-controlled, double-blind cardiovascular outcomes trial. In this trial, 3,297 patients with inadequately controlled type 2 diabetes and atherosclerotic cardiovascular disease were randomized to OZEMPIC (0.5 mg or 1 mg) once weekly or placebo for a minimum observation time of 2 years. The trial compared the risk of Major Adverse Cardiovascular Event (MACE) between semaglutide and placebo when these were added to and used concomitantly with standard of care treatments for diabetes and cardiovascular disease. The primary endpoint, MACE, was the time to first occurrence of a three-part composite outcome which included cardiovascular death, non-fatal myocardial infarction and non-fatal stroke.

Patients eligible to enter the trial were; 50 years of age or older and had established, stable, cardiovascular, cerebrovascular, peripheral artery disease, chronic kidney disease or NYHA class II and III heart failure or were 60 years of age or older and had other specified risk factors for cardiovascular disease. In total, 1,940 patients (58.8%) had established cardiovascular disease without chronic kidney disease, 353 (10.7%) had chronic kidney disease only, and 442 (13.4%) had both cardiovascular disease and kidney disease; 562 patients (17%) had cardiovascular risk factors without established cardiovascular disease or chronic kidney disease. In the trial 453 patients (13.7%) had peripheral artery disease. The mean age at baseline was 65 years, and 61% were men. The mean duration of diabetes was 13.9 years, and mean BMI was 33 kg/m^2. Overall, 83% were White, 7% were Black or African American, and 8% were Asian; 16% identified as Hispanic or Latino ethnicity. Concomitant diseases of patients in this trial included, but were not limited to, heart failure (24%), hypertension (93%), history of ischemic stroke (12%) and history of a myocardial infarction (33%). In total, 98.0% of the patients completed the trial and the vital status was known at the end of the trial for 99.6%.

For the primary analysis, a Cox proportional hazards model was used to test for non-inferiority of OZEMPIC to placebo for time to first MACE using a risk margin of 1.3. The statistical analysis plan pre specified that the 0.5 mg and 1 mg doses would be combined. Type-1 error was controlled across multiple tests using a hierarchical testing strategy.

OZEMPIC significantly reduced the occurrence of MACE. The estimated hazard ratio for time to first MACE

was 0.74 (95% CI: 0.58, 0.95). Refer to Figure 6 and Table 9.

Figure 6. Kaplan-Meier: Time to First Occurrence of a MACE in the SUSTAIN 6 Trial

The treatment effect for the primary composite endpoint and its components in the SUSTAIN 6 trial is shown in Table 9.

Table 9. Treatment Effect for MACE and its Components, Median Study Observation Time of 2.1 Years

 | Placebo N=1649 (%) | OZEMPIC N=1648 (%) | Hazard ratio vs Placebo (95% CI)a
Composite of cardiovascular death, non-fatal myocardial infarction, non-fatal stroke (time to first occurrence) | 146 (8.9) | 108 (6.6) | 0.74 (0.58, 0.95)
Non-fatal Myocardial Infarction | 64 (3.9) | 47 (2.9) | 0.74 (0.51, 1.08)
Non-fatal Stroke | 44 (2.7) | 27 (1.6) | 0.61 (0.38, 0.99)
Cardiovascular Death | 46 (2.8) | 44 (2.7) | 0.98 (0.65, 1.48)
Fatal or Non-fatal Myocardial Infarction | 67 (4.1) | 54 (3.3) | 0.81 (0.57, 1.16)
Fatal or Non-fatal Stroke | 46 (2.8) | 30 (1.8) | 0.65 (0.41, 1.03)

a Cox-proportional hazards models with treatment as factor and stratified by evidence of cardiovascular disease, insulin treatment and renal impairment.

14.3 Kidney Outcomes Trial of OZEMPIC in Adults with Type 2 Diabetes Mellitus and Chronic Kidney Disease

FLOW (NCT03819153) was a randomized, double-blind, placebo-controlled, event driven trial in adults with type 2 diabetes mellitus and chronic kidney disease (eGFR 25 to 75 mL/min/1.73 m^2 with urine albumin-to- creatinine ratio [UACR] >100 mg/g and <5000 mg/g). All patients needed to have an HbA1c ≤10% at screening and be receiving standard of care background therapy, including a maximum tolerated labeled dose of a renin- angiotensin-aldosterone system (RAAS) blocking agent including an angiotensin converting enzyme (ACE) inhibitor or an angiotensin II receptor blocker (ARB), unless such treatment was contraindicated or not tolerated. The trial excluded patients with congenital or hereditary kidney diseases including polycystic kidney disease, autoimmune kidney diseases including glomerulonephritis or congenital urinary tract malformations.

A total of 3,533 patients were randomized to receive OZEMPIC 1 mg once weekly or placebo and were followed for a median of 41 months. The mean age of the study population was 67 years, and 70% of patients were male. Approximately 66% of the trial population was White, 24% Asian, and 5% Black or African American. At baseline, the mean eGFR was 47 mL/min/1.73m^2, with 11% of patients having an eGFR <30 mL/min/1.73m^2. Median baseline UACR was 568 mg/g with 69% of patients with a UACR >300 mg/g. At baseline, 95% of patients were treated with an ACE inhibitor or ARB, 16% were on sodium-glucose cotransporter 2 (SGLT2) inhibitors, 76% were on a statin, and 50% were on an antiplatelet agent.

OZEMPIC was superior to placebo in reducing the incidence of the primary composite endpoint of a sustained decline in eGFR of ≥50%, sustained eGFR <15 mL/min/1.73 m^2, chronic renal replacement therapy, renal death, CV death (HR 0.76 [95% CI 0.66, 0.88], p=0.0003) as shown in Table 10 and Figure 7. The treatment effect reflected a reduction in a sustained decline in eGFR of ≥50%, progression to kidney failure and CV death. There were few renal deaths during the trial.

OZEMPIC also reduced the annual rate of change in eGFR (Figure 9), the incidence of a composite cardiovascular endpoint, consisting of non-fatal myocardial infarction (MI), non-fatal stroke, and cardiovascular death, and the incidence of all-cause death (Table 10 and Figure 8).

The treatment effect on the primary composite endpoint was generally consistent across the pre-specified subgroups examined, including age, biological sex, eGFR and UACR. The treatment benefit on the primary composite endpoint was not evident in patients taking SGLT2 inhibitors at baseline, but there were few events in these patients.

Table 10: Analyses of the Primary and Secondary Endpoints and their Individual Components in FLOW Trial

 | Placebo N=1766 (%) | OZEMPIC 1 mg N=1767 (%) | Hazard ratio vs placebo (95% CI)1 | p-value^2
 | Number of Patients (%)
Composite Endpoint (≥50% sustained eGFR decline, sustained eGFR < 15 mL/min/1.73 m^2, chronic renal replacement therapy, or renal or cardiovascular death (time to first occurrence)^3 | 410 (23.2) | 331 (18.7) | 0.76 (0.66, 0.88) | 0.0003
≥50% sustained eGFR decline^3 | 213 (12.1) | 165 (9.3) | 0.73 (0.59, 0.89)
Sustained eGFR <15mL/min/1.73 m^(2 3) | 110 (6.2) | 92 (5.2) | 0.8 (0.61, 1.06)
Chronic renal replacement therapy | 100 (5.7) | 87 (4.9) | 0.84 (0.63, 1.12)
Renal death | 5 (0.3) | 5 (0.3) | 0.97 (0.27, 3.49)
Cardiovascular death | 169 (9.6) | 123 (7) | 0.71 (0.56, 0.89)
Composite of cardiovascular death, non-fatal myocardial infarction, non-fatal stroke (time to first occurrence) | 254 (14.4) | 212 (12) | 0.82 (0.68, 0.98) | 0.0289
All-cause death | 279 (15.8) | 227 (12.8) | 0.8 (0.67, 0.95) | 0.0104

^1 Cox proportional hazards model with treatment as factor and stratified by baseline use of SGLT2-inhibitor at baseline (yes or no).

^2 Two-sided p-value for the test of no difference. The significance level was 0.03224.

^3 Sustained was defined as having 2 consecutive measurements ≥28 days apart fulfilling the criteria.

Figure 7. Cumulative Incidence: Time to First Occurrence of the Primary Composite Endpoint - Sustained Decline in eGFR ≥50%, Sustained eGFR<15 mL/min/1.73m^2, Chronic Renal Replacement Therapy, Renal Death or CV Death

Cumulative incidence estimates are based on time from randomization to first composite renal event with non-CV and non-renal death modelled as competing risk. The x-axis is truncated at 52 months where approximately 5% of the population was in the trial.

Sustained was defined as having 2 consecutive measurements ≥28 days apart fulfilling the criteria.

Figure 8. Cumulative incidence: Time to First Occurrence of MACE in FLOW Trial

Cumulative incidence estimates are based on time from randomization to first EAC-confirmed MACE with non-CV death modelled as competing risk. The x-axis is truncated at 52 months where approximately 5% of the population was in the trial.

Figure 9. Observed Mean Plot: eGFR (mL/min/1.73m^2) by Week in FLOW Trial

Observed data from the in-trial period until week 104. Error bars are +/- 1.96 *standard error of the mean eGFR, which was calculated using the CKD-EPI 2009 formula.
CKD-EPI: Chronic Kidney Disease Epidemiology Collaboration, eGFR: estimated glomerular filtration rate.

16 HOW SUPPLIED/STORAGE AND HANDLING

How Supplied

Injection: clear, colorless solution of 0.68 mg/mL, 1.34 mg/mL or 2.68 mg/mL of semaglutide available in prefilled, disposable, single-patient-use pens in the following packaging configurations:

Dose per Injection | Use For | Total Strength per Total Volume | Doses per Pen | Carton Contents | NDC
0.25 mg; 0.5 mg | Initiation; Maintenance | 2 mg/3 mL | 4 doses of 0.25 mg and; 2 doses of 0.5 mg; or; 4 doses of 0.5 mg | 1 pen; 6 NovoFine® Plus needles | 0169-4181-13
1 mg | Maintenance | 4 mg/3 mL | 4 doses of 1 mg | 1 pen; 4 NovoFine® Plus needles | 0169-4130-13
2 mg | Maintenance | 8 mg/3 mL | 4 doses of 2 mg | 1 pen; 4 NovoFine® Plus needles | 0169-4772-12

The 2 mg/1.5 mL (1.34 mg/mL) strength (NDC 0169-4132-12) is not currently marketed by Novo Nordisk Inc.

Each OZEMPIC pen is for use by a single patient. An OZEMPIC pen must never be shared between patients, even if the needle is changed [see Warnings and Precautions (5.4)].

Recommended Storage

Prior to first use, OZEMPIC should be stored in a refrigerator between 36ºF to 46ºF (2ºC to 8ºC). Do not store in the freezer or directly adjacent to the refrigerator cooling element. Do not freeze OZEMPIC and do not use OZEMPIC if it has been frozen.

After first use of the OZEMPIC pen, the pen can be stored for 56 days at controlled room temperature 59°F to 86°F (15°C to 30°C) or in a refrigerator 36°F to 46°F (2°C to 8°C). Do not freeze. Keep the pen cap on when not in use. OZEMPIC should be protected from excessive heat and sunlight.

Always remove and safely discard the needle after each injection and store the OZEMPIC pen without an injection needle attached. Always use a new needle for each injection.

Recommended Storage Conditions for the OZEMPIC Pen

Prior to first use | After first use
Refrigerated; 36°F to 46°F; (2°C to 8°C) | Room Temperature; 59°F to 86°F; (15°C to 30°C) | Refrigerated; 36°F to 46°F; (2°C to 8°C)
Until expiration date | 56 days

17 PATIENT COUNSELING INFORMATION

Advise the patient to read the FDA-approved patient labeling (Medication Guide and Instructions for Use).

Risk of Thyroid C-cell Tumors

Inform patients that semaglutide causes thyroid C-cell tumors in rodents and that the human relevance of this finding has not been determined. Counsel patients to report symptoms of thyroid tumors (e.g., a lump in the neck, hoarseness, dysphagia, or dyspnea) to their physician [see Boxed Warning, Warnings and Precautions (5.1)].

Acute Pancreatitis

Inform patients of the potential risk for acute pancreatitis and its symptoms: severe abdominal pain that may radiate to the back, and which may or may not be accompanied by nausea or vomiting. Instruct patients to discontinue OZEMPIC promptly and contact their physician if pancreatitis is suspected [see Warnings and Precautions (5.2)].

Diabetic Retinopathy Complications

Inform patients to contact their physician if changes in vision are experienced during treatment with OZEMPIC [see Warnings and Precautions (5.3)].

Never Share an OZEMPIC Pen Between Patients

Advise patients that they must never share an OZEMPIC pen with another person, even if the needle is changed, because doing so carries a risk for transmission of blood-borne pathogens [see Warnings and Precautions (5.4)].

Hypoglycemia with Concomitant Use of Insulin Secretagogues or Insulin

Inform patients that the risk of hypoglycemia is increased when OZEMPIC is used with an insulin secretagogue (such as a sulfonylurea) or insulin. Educate patients on the signs and symptoms of hypoglycemia [see Warnings and Precautions (5.5)].

Acute Kidney Injury Due to Volume Depletion

Inform patients of the potential risk of acute kidney injury due to dehydration associated with gastrointestinal adverse reactions. Advise patients to take precautions to avoid fluid depletion. Inform patients of the signs and symptoms of acute kidney injury and instruct them to promptly report any of these signs or symptoms or persistent (or extended) nausea, vomiting, and diarrhea to their healthcare provider [see Warnings and Precautions (5.6)].

Severe Gastrointestinal Adverse Reactions

Inform patients of the potential risk of severe gastrointestinal adverse reactions. Instruct patients to contact their healthcare provider if they have severe or persistent gastrointestinal symptoms [see Warnings and Precautions (5.7)]

Hypersensitivity Reactions

Inform patients that serious hypersensitivity reactions have been reported during postmarketing use of OZEMPIC. Advise patients on the symptoms of hypersensitivity reactions and instruct them to stop taking OZEMPIC and seek medical advice promptly if such symptoms occur [see Warnings and Precautions (5.8)].

Acute Gallbladder Disease

Inform patients of the potential risk for cholelithiasis or cholecystitis. Instruct patients to contact their physician if cholelithiasis or cholecystitis is suspected for appropriate clinical follow-up [see Warnings and Precautions (5.9)].

Pulmonary Aspiration During General Anesthesia or Deep Sedation

Inform patients that OZEMPIC may cause their stomach to empty more slowly which may lead to complications with anesthesia or deep sedation during planned surgeries or procedures. Instruct patients to inform healthcare providers prior to any planned surgeries or procedures if they are taking OZEMPIC [see Warnings and Precautions (5.10)].

Pregnancy

Advise a pregnant woman of the potential risk to a fetus. Advise women to inform their healthcare provider if they are pregnant or intend to become pregnant [see Use in Specific Populations (8.1, 8.3)].

Missed doses

Inform patients if a dose is missed, it should be administered as soon as possible within 5 days after the missed dose. If more than 5 days have passed, the missed dose should be skipped and the next dose should be administered on the regularly scheduled day. In each case, inform patients to resume their regular once-weekly dosing schedule [see Dosage and Administration (2.1)].

Manufactured by:

Novo Nordisk A/S

DK-2880 Bagsvaerd

Denmark

For information about OZEMPIC contact:

Novo Nordisk Inc.

800 Scudders Mill Road

Plainsboro, NJ 08536

1-888-693-6742

OZEMPIC® and NovoFine® are registered trademarks of Novo Nordisk A/S.

Patent Information: http://www.novonordisk-us.com/products/product-patents.html

© 2025 Novo Nordisk

Medication Guide

OZEMPIC® (oh-ZEM-pick)

(semaglutide)

injection, for subcutaneous use

Do not share your OZEMPIC pen with other people, even if the needle has been changed. You may give other people a serious infection, or get a serious infection from them.

Read this Medication Guide before you start using OZEMPIC and each time you get a refill. There may be new information. This information does not take the place of talking to your healthcare provider about your medical condition or your treatment.

What is the most important information I should know about OZEMPIC?

OZEMPIC may cause serious side effects, including:

- Possible thyroid tumors, including cancer. Tell your healthcare provider if you get a lump or swelling in your neck, hoarseness, trouble swallowing, or shortness of breath. These may be symptoms of thyroid cancer. In studies with rodents, OZEMPIC and medicines that work like OZEMPIC caused thyroid tumors, including thyroid cancer. It is not known if OZEMPIC will cause thyroid tumors or a type of thyroid cancer called medullary thyroid carcinoma (MTC) in people.
- Do not use OZEMPIC if you or any of your family have ever had a type of thyroid cancer called medullary thyroid carcinoma (MTC), or if you have an endocrine system condition called Multiple Endocrine Neoplasia syndrome type 2 (MEN 2).

What is OZEMPIC?

OZEMPIC is an injectable prescription medicine used:

- along with diet and exercise to improve blood sugar (glucose) in adults with type 2 diabetes mellitus.
- to reduce the risk of major cardiovascular events such as heart attack, stroke or death in adults with type 2 diabetes mellitus with known heart disease.
- to reduce the risk of kidney disease worsening, kidney failure (end-stage kidney disease), and death due to cardiovascular disease in adults with type 2 diabetes mellitus and chronic kidney disease.

It is not known if OZEMPIC is safe and effective for use in children.

Do not use OZEMPIC if:

- you or any of your family have ever had a type of thyroid cancer called medullary thyroid carcinoma (MTC) or if you have an endocrine system condition called Multiple Endocrine Neoplasia syndrome type 2 (MEN 2).
- you have had a serious allergic reaction to semaglutide or any of the ingredients in OZEMPIC. See the end of this Medication Guide for a complete list of ingredients in OZEMPIC. See “What are the possible side effects of OZEMPIC?” for symptoms of a serious allergic reaction.

Before using OZEMPIC, tell your healthcare provider if you have any other medical conditions, including if you:

- have or have had problems with your pancreas.
- have a history of diabetic retinopathy.
- have severe problems with your stomach, such as slowed emptying of your stomach (gastroparesis) or problems with digesting food.
- are scheduled to have surgery or other procedures that use anesthesia or deep sleepiness (deep sedation).
- are pregnant or plan to become pregnant. It is not known if OZEMPIC will harm your unborn baby. You should stop using OZEMPIC at least 2 months before you plan to become pregnant. Talk to your healthcare provider about the best way to control your blood sugar if you plan to become pregnant or while you are pregnant.
- are breastfeeding or plan to breastfeed. It is not known if OZEMPIC passes into your breast milk. You should talk with your healthcare provider about the best way to feed your baby while using OZEMPIC.
Tell your healthcare provider about all the medicines you take, including prescription and over-the-counter medicines, vitamins, and herbal supplements. OZEMPIC may affect the way some medicines work and some medicines may affect the way OZEMPIC works.
Before using OZEMPIC, talk to your healthcare provider about low blood sugar and how to manage it. Tell your healthcare provider if you are taking other medicines to treat diabetes, including insulin or sulfonylureas.

Know the medicines you take. Keep a list of them to show your healthcare provider and pharmacist when you get a new medicine.

How should I use OZEMPIC?

- Read the Instructions for Use that comes with OZEMPIC.
- Use OZEMPIC exactly as your healthcare provider tells you to.
- Your healthcare provider should show you how to use OZEMPIC before you use it for the first time.
- OZEMPIC is injected under the skin (subcutaneously) of your stomach (abdomen), thigh, or upper arm. Do not inject OZEMPIC into a muscle (intramuscularly) or vein (intravenously).
- Use OZEMPIC 1 time each week, on the same day each week, at any time of the day.
- You may change the day of the week you use OZEMPIC as long as your last dose was given 2 or more days before.
- If you miss a dose of OZEMPIC, take the missed dose as soon as possible within 5 days after the missed dose. If more than 5 days have passed, skip the missed dose and take your next dose on the regularly scheduled day.
- OZEMPIC may be taken with or without food.
- Do not mix insulin and OZEMPIC together in the same injection.
- You may give an injection of OZEMPIC and insulin in the same body area (such as your stomach area), but not right next to each other.
- Change (rotate) your injection site with each injection. Do not use the same site for each injection.
- Do not share your OZEMPIC pen with other people, even if the needle has been changed. You may give other people a serious infection, or get a serious infection from them.
- If you take too much OZEMPIC, call your healthcare provider or Poison Help line at 1-800-222-1222 or go to the nearest hospital emergency room right away.

What are the possible side effects of OZEMPIC?

OZEMPIC may cause serious side effects, including:

- See “What is the most important information I should know about OZEMPIC?”
- inflammation of your pancreas (pancreatitis). Stop using OZEMPIC and call your healthcare provider right away if you have severe pain in your stomach area (abdomen) that will not go away, with or without vomiting. You may feel the pain from your abdomen to your back.
- changes in vision. Tell your healthcare provider if you have changes in vision during treatment with OZEMPIC.
- low blood sugar (hypoglycemia). Your risk for getting low blood sugar may be higher if you use OZEMPIC with another medicine that can cause low blood sugar, such as a sulfonylurea or insulin. Signs and symptoms of low blood sugar may include:

- dizziness or light-headedness

- blurred vision

- anxiety, irritability, or mood changes

- sweating

- slurred speech

- hunger

- confusion or drowsiness

- shakiness

- weakness

- headache

- fast heartbeat

- feeling jittery

- Dehydration leading to kidney problems. Diarrhea, nausea, and vomiting may cause a loss of fluids (dehydration) which may cause kidney problems. It is important for you to drink fluids to help reduce your chance of dehydration. Tell your healthcare provider right away if you have nausea, vomiting, or diarrhea that does not go away.
- Severe stomach problems. Stomach problems, sometimes severe, have been reported in people who use OZEMPIC. Tell your healthcare provider if you have stomach problems that are severe or will not go away.
- serious allergic reactions. Stop using OZEMPIC and get medical help right away, if you have any symptoms of a serious allergic reaction including:
  - swelling of your face, lips, tongue or throat
  - problems breathing or swallowing
  - severe rash or itching
  - fainting or feeling dizzy
  - very rapid heartbeat
- gallbladder problems. Gallbladder problems have happened in some people who take OZEMPIC. Tell your healthcare provider right away if you get symptoms of gallbladder problems which may include:

- pain in your upper stomach (abdomen)

- yellowing of skin or eyes (jaundice)

- fever

- clay-colored stools

- food or liquid getting into the lungs during surgery or other procedures that use anesthesia or deep sleepiness (deep sedation). OZEMPIC may increase the chance of food getting into your lungs during surgery or other procedures. Tell all your healthcare providers that you are taking OZEMPIC before you are scheduled to have surgery or other procedures.

The most common side effects of OZEMPIC may include nausea, vomiting, diarrhea, stomach (abdominal) pain, and constipation.

Talk to your healthcare provider about any side effect that bothers you or does not go away. These are not all the possible side effects of OZEMPIC.

Call your doctor for medical advice about side effects. You may report side effects to FDA at 1‑800‑FDA‑1088.

General information about the safe and effective use of OZEMPIC.

Medicines are sometimes prescribed for purposes other than those listed in a Medication Guide. Do not use OZEMPIC for a condition for which it was not prescribed. Do not give OZEMPIC to other people, even if they have the same symptoms that you have. It may harm them.

You can ask your pharmacist or healthcare provider for information about OZEMPIC that is written for health professionals.

What are the ingredients in OZEMPIC?

Active Ingredient: semaglutide

Inactive Ingredients: disodium phosphate dihydrate, propylene glycol, phenol and water for injection. Hydrochloric acid or sodium hydroxide may be added to adjust pH.

Manufactured by: Novo Nordisk A/S, DK-2880 Bagsvaerd, Denmark

OZEMPIC® is a registered trademark of Novo Nordisk A/S.

PATENT Information: http://novonordisk-us.com/products/product-patents.html

© 2025 Novo Nordisk

For more information, go to OZEMPIC.com or call 1-888-693-6742.

This Medication Guide has been approved by the U.S. Food and Drug Administration. Revised: 01/2025

Instructions for Use - 0.25 mg or 0.5 mg doses, 2 mg/3 mL pen

INSTRUCTIONS FOR USE

OZEMPIC® [oh-ZEM-pick]

(semaglutide)

injection, for subcutaneous use

0.25 mg or 0.5 mg doses

(pen delivers doses in 0.25 mg or 0.5 mg increments only)

- Read these instructions carefully before using your OZEMPIC® pen.
- Do not use your pen without proper training from your healthcare provider. Make sure that you know how to give yourself an injection with the pen before you start your treatment.
- Do not share your OZEMPIC pen with other people, even if the needle has been changed. You may give other people a serious infection, or get a serious infection from them.

If you are blind or have poor eyesight and cannot read the dose counter on the pen, do not use this pen without help. Get help from a person with good eyesight who is trained to use the OZEMPIC pen.

- Start by checking your pen to make sure that it contains OZEMPIC, then look at the pictures below to get to know the different parts of your pen and needle.
- Your pen is a prefilled, single-patient-use, dial-a-dose pen. It contains 2 mg of semaglutide, and you can select doses of 0.25 mg or 0.5 mg. Each prefilled pen contains 4 doses of 0.25 mg and 2 doses of 0.5 mg or contains 4 doses of 0.5 mg.
- Your pen is made to be used with NovoFine® Plus or NovoFine® disposable needles up to a length of 8 mm.
- NovoFine® Plus 32G 4 mm disposable needles are included with your OZEMPIC pen.
- Always use a new needle for each injection.

Supplies you will need to give your OZEMPIC injection:

- OZEMPIC pen
- a new NovoFine Plus or NovoFine needle
- 1 alcohol swab
- 1 gauze pad or cotton ball
- 1 sharps disposal container for throwing away used OZEMPIC pens and needles. See “Disposing of used OZEMPIC pens and needles” at the end of these instructions.

Step 1.

Prepare your pen with a new needle

- Wash your hands with soap and water.
- Check the name and colored label of your pen, to make sure that it contains OZEMPIC.
This is especially important if you take more than 1 type of medicine.
- Pull off the pen cap.

- Check that the OZEMPIC medicine in your pen is clear and colorless.
Look through the pen window. If OZEMPIC looks cloudy or contains particles, do not use the pen.

- Take a new needle, and tear off the paper tab. Do not attach a new needle to your pen until you are ready to give your injection.

- Push the needle straight onto the pen. Turn until it is on tight.

- The needle is covered by 2 caps. You must remove both caps. If you forget to remove both caps, you will not inject any medicine.
- Pull off the outer needle cap. Do not throw it away.

- Pull off the inner needle cap and throw it away.
A drop of OZEMPIC may appear at the needle tip. This is normal, but you must still check the OZEMPIC flow if you use a new pen for the first time.

Always use a new needle for each injection. This will reduce the risk of contamination, infection, leakage of OZEMPIC, and blocked needles leading to the wrong dose.

Do not reuse or share your needles with other people. You may give other people a serious infection, or get a serious infection from them.

Never use a bent or damaged needle.

Step 2.

First Time Use for Each New Pen: Check the OZEMPIC flow

- Check the OZEMPIC flow before the first injection with each new pen only.
If your OZEMPIC pen is already in use, go to Step 3 “Select your dose”.
- Turn the dose selector until the dose counter shows the flow check symbol ().

- Hold the pen with the needle pointing up.
Press and hold in the dose button until the dose counter shows 0. The 0 must line up with the dose pointer.
A drop of OZEMPIC will appear at the needle tip.
- If no drop appears, repeat Step 2 above as shown in Figure G and Figure H up to 6 times. If there is still no drop, change the needle and repeat Step 2 as shown in Figure G and Figure H 1 more time.
Do not use the pen if a drop of OZEMPIC still does not appear.
Contact Novo Nordisk at 1-888-693-6742.

Always make sure that a drop appears at the needle tip before you use a new pen for the first time. This makes sure that OZEMPIC flows.

If no drop appears, you will not inject any OZEMPIC, even though the dose counter may move. This may mean that there is a blocked or damaged needle.

A small drop may remain at the needle tip, but it will not be injected.

Only check the OZEMPIC flow before your first injection with each new pen.

Step 3.

Select your dose

- Turn the dose selector until the dose counter stops and shows your dose (0.25 mg or 0.5 mg).
The dashed line in the dose counter will guide
you to your dose.
Make sure you know the dose of OZEMPIC you should use. If you select the wrong dose, you can turn the dose selector forward or backwards to the correct dose.

Always use the dose counter and the dose pointer to see how many mg you select.

You will hear a “click” every time you turn the dose selector. Do not set the dose by counting the number of clicks you hear.

Only doses of 0.25 mg or 0.5 mg can be selected with the dose selector. The selected dose must line up exactly with the dose pointer to make sure that you get a correct dose.

The dose selector changes the dose. Only the dose counter and dose pointer will show how many mg you select for each dose.

You can select 0.25 mg or 0.5 mg for each dose. When your pen contains less than 0.5 or 0.25 mg, the dose counter stops before 0.5 mg or 0.25 mg is shown.

The dose selector clicks differently when turned forward or backward. Do not count the pen clicks.

How much OZEMPIC is left?

- To see how much OZEMPIC is left in your pen, use the dose counter:
Turn the dose selector until the dose counter stops.
- If it shows 0.5, at least 0.5 mg is left in your pen. If the dose counter stops before 0.5 mg, there is not enough OZEMPIC left for a full dose of 0.5 mg.
- If it shows 0.25, at least 0.25 mg is left in your pen. If the dose counter stops before 0.25 mg, there is not enough OZEMPIC left for a full dose of 0.25 mg.
If there is not enough OZEMPIC left in your pen for a full dose, do not use it. Use a new OZEMPIC pen.

Step 4.

Inject your dose

- Choose your injection site and wipe the skin with an alcohol swab. Let the injection site dry before you inject your dose (See Figure K).

- Insert the needle into your skin as your healthcare provider has shown you.
- Make sure you can see the dose counter. Do not cover it with your fingers. This could stop the injection.

- Press and hold down the dose button until the dose counter shows 0.
The 0 must line up with the dose pointer. You may then hear or feel a click.
Continue pressing the dose button while keeping the needle in your skin.

- Count 6 seconds while keeping the dose button pressed.
- If the needle is removed earlier, you may see a stream of OZEMPIC coming from the needle tip. If this happens, the full dose will not be delivered.

- Remove the needle from your skin. You can then release the dose button.
If blood appears at the injection site, press lightly with a gauze pad or cotton ball. Do not rub the area.

Always watch the dose counter to make sure you have injected your complete dose. Hold the dose button down until the dose counter shows 0.

How to identify a blocked or damaged needle?

- If 0 does not appear in the dose counter after continuously pressing the dose button, you may have used a blocked or damaged needle.
- If this happens you have not received any OZEMPIC even though the dose counter has moved from the original dose that you have set.

How to handle a blocked needle?

Change the needle as described in Step 5, and repeat all steps starting with Step 1: “Prepare your pen with a new needle”.

Never touch the dose counter when you inject. This can stop the injection.

You may see a drop of OZEMPIC at the needle tip after injecting. This is normal and does not affect your dose.

Step 5.

After your injection

- Carefully remove the needle from the pen. Do not put the needle caps back on the needle to avoid needle sticks.

- Place the needle in a sharps disposal container right away to reduce the risk of needle sticks. See “Disposing of used OZEMPIC pens and needles” below for more information about how to dispose of used pens and needles the right way.

- Put the pen cap on your pen after each use to protect OZEMPIC from light.

- If you do not have a sharps disposal container, follow a 1-handed needle recapping method. Carefully slip the needle into the outer needle cap. Dispose of the needle in a sharps disposal container as soon as possible.

Never try to put the inner needle cap back on the needle. You may stick yourself with the needle.

Always remove the needle from your pen.

This will reduce the risk of contamination, infection, leakage of OZEMPIC, and blocked needles leading to the wrong dose. If the needle is blocked, you will not inject any OZEMPIC.

Always dispose of the needle after each injection.

Disposing of used OZEMPIC pens and needles:

- Put your used OZEMPIC pen and needle in a FDA-cleared sharps disposal container right away after use.
- If you do not have a FDA-cleared sharps disposal container, you may use a household container that is:
  - made of a heavy-duty plastic
  - can be closed with a tight-fitting, puncture-resistant lid, without sharps being able to come out
  - upright and stable during use
  - leak-resistant
  - properly labeled to warn of hazardous waste inside the container
- When your sharps disposal container is almost full, you will need to follow your community guidelines for the right way to dispose of your sharps disposal container. There may be state or local laws about how you should throw away used needles and syringes. For more information about the safe sharps disposal, and for specific information about sharps disposal in the state that you live in, go to the FDA’s website at: http://www.fda.gov/safesharpsdisposal
- Do not dispose of your used sharps disposal container in your household trash unless your community guidelines permit this. Do not recycle your used sharps disposal container.
- Safely dispose of OZEMPIC that is out of date or no longer needed.

Important

- Caregivers must be very careful when handling used needles to prevent accidental needle stick injuries and prevent passing (transmission) of infection.
- Never use a syringe to withdraw OZEMPIC from your pen.
- Always carry an extra pen and new needles with you, in case of loss or damage.
- Always keep your pen and needles out of reach of others, especially children.
- Always keep your pen with you. Do not leave it in a car or other place where it can get too hot or too cold.

Caring for your pen

- Do not drop your pen or knock it against hard surfaces. If you drop it or suspect a problem, attach a new needle and check the OZEMPIC flow before you inject.
- Do not try to repair your pen or pull it apart.
- Do not expose your pen to dust, dirt or liquid.
- Do not wash, soak, or lubricate your pen. If necessary, clean it with mild detergent on a moistened cloth.

How should I store my OZEMPIC pen?

- Store your new, unused OZEMPIC pens in the refrigerator between 36°F to 46°F (2°C to 8°C).
- Store your pen in use for 56 days at room temperature between 59ºF to 86ºF (15ºC to 30ºC) or in a refrigerator between 36°F to 46°F (2°C to 8°C).
- The OZEMPIC pen you are using should be disposed of (thrown away) after 56 days, even if it still has OZEMPIC left in it. Write the disposal date on your calendar.
- Do not freeze OZEMPIC. Do not use OZEMPIC if it has been frozen.
- Unused OZEMPIC pens may be used until the expiration date (“EXP”) printed on the label, if kept in the refrigerator.
- When stored in the refrigerator, do not store OZEMPIC pens directly next to the cooling element.
- Keep OZEMPIC away from heat and out of the light.
- Keep the pen cap on when not in use.
- Keep OZEMPIC and all medicines out of the reach of children.

For more information go towww.OZEMPIC.com

Manufactured by:

Novo Nordisk A/S

DK-2880 Bagsvaerd

Denmark

For information about OZEMPIC contact:

Novo Nordisk Inc.

800 Scudders Mill Road

Plainsboro, NJ 08536

1-888-693-6742

Version: 2

OZEMPIC® and NovoFine® are registered trademarks of Novo Nordisk A/S.

PATENT Information: https://www.novonordisk-us.com/products/product-patents.html

© 2023 Novo Nordisk

This Instructions for Use has been approved by the U.S. Food and Drug Administration.

Revised: September 2023

Instructions for Use – 1 mg dose, 3 mL pen

INSTRUCTIONS FOR USE

OZEMPIC® [oh-ZEM-pick]

(semaglutide)

injection, for subcutaneous use

1 mg dose

(pen delivers doses in 1 mg increments only)

- Read these instructions carefully before using your OZEMPIC® pen.
- Do not use your pen without proper training from your healthcare provider. Make sure that you know how to give yourself an injection with the pen before you start your treatment.
- Do not share your OZEMPIC pen with other people, even if the needle has been changed. You may give other people a serious infection, or get a serious infection from them.

If you are blind or have poor eyesight and cannot read the dose counter on the pen, do not use this pen without help. Get help from a person with good eyesight who is trained to use the OZEMPIC pen.

- Start by checking your pen to make sure that it contains OZEMPIC, then look at the pictures below to get to know the different parts of your pen and needle.
- Your pen is a prefilled, single-patient-use, dial-a-dose pen. It contains 4 mg of semaglutide, and you can only select doses of 1 mg. Each prefilled pen contains 4 doses of 1 mg.
- Your pen is made to be used with NovoFine® Plus or NovoFine® disposable needles up to a length of 8 mm.
- NovoFine® Plus 32G 4 mm disposable needles are included with your OZEMPIC pen.
- Always use a new needle for each injection.

Supplies you will need to give your OZEMPIC injection:

- OZEMPIC pen 1 mg dose
- a new NovoFine Plus or NovoFine needle
- 1 alcohol swab
- 1 gauze pad or cotton ball
- 1 sharps disposal container for throwing away used OZEMPIC pens and needles.
See “Disposing of used OZEMPIC pens and needles” at the end of these instructions.

Step 1.

Prepare your pen with a new needle

- Wash your hands with soap and water.
- Check the name and colored label of your pen, to make sure that it contains OZEMPIC.
This is especially important if you take more than 1 type of medicine.
- Pull off the pen cap.

- Check that the OZEMPIC medicine in your pen is clear and colorless.
Look through the pen window. If OZEMPIC looks cloudy or contains particles, do not use the pen.

- Take a new needle, and tear off the paper tab.
Do not attach a new needle to your pen until you are ready to give your injection.

- Push the needle straight onto the pen. Turn until it is on tight.

- The needle is covered by 2 caps. You must remove both caps. If you forget to remove both caps, you will not inject any medicine.
- Pull off the outer needle cap. Do not throw it away.

- Pull off the inner needle cap and throw it away.
A drop of OZEMPIC may appear at the needle tip. This is normal, but you must still check the OZEMPIC flow if you use a new pen for the first time.

Always use a new needle for each injection. This will reduce the risk of contamination, infection, leakage of OZEMPIC, and blocked needles leading to the wrong dose.

Do not reuse or share your needles with other people. You may give other people a serious infection, or get a serious infection from them.

Never use a bent or damaged needle.

Step 2.

First Time Use for Each New Pen: Check the OZEMPIC flow

- Check the OZEMPIC flow before the first injection with each new pen only.
If your OZEMPIC pen is already in use, go to Step 3 “Select your dose”.
- Turn the dose selector until the dose counter shows the flow check symbol ().

- Hold the pen with the needle pointing up.
Press and hold in the dose button until the dose counter shows 0. The 0 must line up with the dose pointer.
A drop of OZEMPIC will appear at the needle tip.
- If no drop appears, repeat Step 2 above as shown in Figure G and Figure H up to 6 times. If there is still no drop, change the needle and repeat Step 2 as shown in Figure G and Figure H 1 more time.
Do not use the pen if a drop of OZEMPIC still does not appear.
Contact Novo Nordisk at 1-888-693-6742.

Always make sure that a drop appears at the needle tip before you use a new pen for the first time. This makes sure that OZEMPIC flows.

If no drop appears, you will not inject any OZEMPIC, even though the dose counter may move. This may mean that there is a blocked or damaged needle.

A small drop may remain at the needle tip, but it will not be injected.

Only check the OZEMPIC flow before your first injection with each new pen.

Step 3.

Select your dose

- Turn the dose selector until the dose counter stops and shows your 1 mg dose.
The dashed line in the dose counter will guide you to 1 mg.

Always use the dose counter and the dose pointer to see that 1 mg has been selected.

You will hear a “click” every time you turn the dose selector. Do not set the dose by counting the number of clicks you hear.

Only doses of 1 mg can be selected with the dose selector. 1 mg must line up exactly with the dose pointer to make sure that you get a correct dose.

The dose selector changes the dose. Only the dose counter and dose pointer will show that 1 mg has been selected.

You can only select 1 mg for each dose. When your pen contains less than 1 mg, the dose counter stops before 1 mg is shown.

The dose selector clicks differently when turned forward or backward. Do not count the pen clicks.

How much OZEMPIC is left?

- To see how much OZEMPIC is left in your pen, use the dose counter:
Turn the dose selector until the dose counter stops.
- If it shows 1, at least 1 mg is left in your pen. If the dose counter stops before 1 mg, there is not enough OZEMPIC left for a full dose of 1 mg.
If there is not enough OZEMPIC left in your pen for a full dose, do not use it. Use a new OZEMPIC pen.

Step 4.

Inject your dose

- Choose your injection site and wipe the skin with an alcohol swab. Let the injection site dry before you inject your dose (See Figure K).

- Insert the needle into your skin as your healthcare provider has shown you.
- Make sure you can see the dose counter. Do not cover it with your fingers. This could stop the injection.

- Press and hold down the dose button until the dose counter shows 0.
The 0 must line up with the dose pointer. You may then hear or feel a click.
Continue pressing the dose button while keeping the needle in your skin.

- Count 6 seconds while keeping the dose button pressed.
- If the needle is removed earlier, you may see a stream of OZEMPIC coming from the needle tip. If this happens, the full dose will not be delivered.

- Remove the needle from your skin. You can then release the dose button.
If blood appears at the injection site, press lightly with a gauze pad or cotton ball. Do not rub the area.

Always watch the dose counter to make sure you have injected your complete dose. Hold the dose button down until the dose counter shows 0.

How to identify a blocked or damaged needle?

- If 0 does not appear in the dose counter after continuously pressing the dose button, you may have used a blocked or damaged needle.
- If this happens you have not received any OZEMPIC even though the dose counter has moved from the original dose that you have set.

How to handle a blocked needle?

Change the needle as described in Step 5, and repeat all steps starting with Step 1: “Prepare your pen with a new needle”.

Never touch the dose counter when you inject. This can stop the injection.

You may see a drop of OZEMPIC at the needle tip after injecting. This is normal and does not affect your dose.

Step 5.

After your injection

- Carefully remove the needle from the pen. Do not put the needle caps back on the needle to avoid needle sticks.

- Place the needle in a sharps disposal container right away to reduce the risk of needle sticks. See “Disposing of used OZEMPIC pens and needles” below for more information about how to dispose of used pens and needles the right way.

- Put the pen cap on your pen after each use to protect OZEMPIC from light.

- If you do not have a sharps disposal container, follow a 1-handed needle recapping method. Carefully slip the needle into the outer needle cap. Dispose of the needle in a sharps disposal container as soon as possible.

Never try to put the inner needle cap back on the needle. You may stick yourself with the needle.

Always remove the needle from your pen.

This will reduce the risk of contamination, infection, leakage of OZEMPIC, and blocked needles leading to the wrong dose. If the needle is blocked, you will not inject any OZEMPIC.

Always dispose of the needle after each injection.

Disposing of used OZEMPIC pens and needles:

- Put your used OZEMPIC pen and needle in a FDA-cleared sharps disposal container right away after use.
- If you do not have a FDA-cleared sharps disposal container, you may use a household container that is:
  - made of a heavy-duty plastic
  - can be closed with a tight-fitting, puncture-resistant lid, without sharps being able to come out
  - upright and stable during use
  - leak-resistant
  - properly labeled to warn of hazardous waste inside the container
- When your sharps disposal container is almost full, you will need to follow your community guidelines for the right way to dispose of your sharps disposal container. There may be state or local laws about how you should throw away used needles and syringes. For more information about the safe sharps disposal, and for specific information about sharps disposal in the state that you live in, go to the FDA’s website at: http://www.fda.gov/safesharpsdisposal
- Do not dispose of your used sharps disposal container in your household trash unless your community guidelines permit this. Do not recycle your used sharps disposal container.
- Safely dispose of OZEMPIC that is out of date or no longer needed.

Important

- Caregivers must be very careful when handling used needles to prevent accidental needle stick injuries and prevent passing (transmission) of infection.
- Never use a syringe to withdraw OZEMPIC from your pen.
- Always carry an extra pen and new needles with you, in case of loss or damage.
- Always keep your pen and needles out of reach of others, especially children.
- Always keep your pen with you. Do not leave it in a car or other place where it can get too hot or too cold.

Caring for your pen

- Do not drop your pen or knock it against hard surfaces. If you drop it or suspect a problem, attach a new needle and check the OZEMPIC flow before you inject.
- Do not try to repair your pen or pull it apart.
- Do not expose your pen to dust, dirt or liquid.
- Do not wash, soak, or lubricate your pen. If necessary, clean it with mild detergent on a moistened cloth.

How should I store my OZEMPIC pen?

- Store your new, unused OZEMPIC pens in the refrigerator between 36°F to 46°F (2°C to 8°C).
- Store your pen in use for 56 days at room temperature between 59ºF to 86ºF (15ºC to 30ºC) or in a refrigerator between 36°F to 46°F (2°C to 8°C).
- The OZEMPIC pen you are using should be disposed of (thrown away) after 56 days, even if it still has OZEMPIC left in it. Write the disposal date on your calendar.
- Do not freeze OZEMPIC. Do not use OZEMPIC if it has been frozen.
- Unused OZEMPIC pens may be used until the expiration date (“EXP”) printed on the label, if kept in the refrigerator.
- When stored in the refrigerator, do not store OZEMPIC pens directly next to the cooling element.
- Keep OZEMPIC away from heat and out of the light.
- Keep the pen cap on when not in use.
- Keep OZEMPIC and all medicines out of the reach of children.

For more information go to www.OZEMPIC.com

Manufactured by:

Novo Nordisk A/S

DK-2880 Bagsvaerd

Denmark

For information about OZEMPIC contact:

Novo Nordisk Inc.

800 Scudders Mill Road

Plainsboro, NJ 08536

1-888-693-6742

Version: 4

OZEMPIC® and NovoFine® are registered trademarks of Novo Nordisk A/S.

PATENT Information: https://www.novonordisk-us.com/products/product-patents.html

© 2023 Novo Nordisk

This Instructions for Use has been approved by the U.S. Food and Drug Administration.

Revised: September 2023

Instructions for Use – 2 mg dose, 3 mL pen

INSTRUCTIONS FOR USE

OZEMPIC® [oh-ZEM-pick]

(semaglutide)

injection, for subcutaneous use

2 mg dose

(pen delivers doses in 2 mg increments only)

- Read these instructions carefully before using your OZEMPIC® pen.
- Do not use your pen without proper training from your healthcare provider. Make sure that you know how to give yourself an injection with the pen before you start your treatment.
- Do not share your OZEMPIC pen with other people, even if the needle has been changed. You may give other people a serious infection, or get a serious infection from them.

If you are blind or have poor eyesight and cannot read the dose counter on the pen, do not use this pen without help. Get help from a person with good eyesight who is trained to use the OZEMPIC pen.

- Start by checking your pen to make sure that it contains OZEMPIC, then look at the pictures below to get to know the different parts of your pen and needle.
- Your pen is a prefilled, single-patient-use, dial-a-dose pen. It contains 8 mg of semaglutide, and you can only select doses of 2 mg. Each prefilled pen contains 4 doses of 2 mg.
- Your pen is made to be used with NovoFine® Plus or NovoFine® disposable needles up to a length of 8 mm.
- NovoFine® Plus 32G 4 mm disposable needles are included with your OZEMPIC pen.
- Always use a new needle for each injection.

Supplies you will need to give your OZEMPIC injection:

- OZEMPIC pen 2 mg dose
- a new NovoFine Plus or NovoFine needle
- 1 alcohol swab
- 1 gauze pad or cotton ball
- 1 sharps disposal container for throwing away used OZEMPIC pens and needles.
See “Disposing of used OZEMPIC pens and needles” at the end of these instructions.

Step 1.

Prepare your pen with a new needle

- Wash your hands with soap and water.
- Check the name and colored label of your pen, to make sure that it contains OZEMPIC.
This is especially important if you take more than 1 type of medicine.
- Pull off the pen cap.

- Check that the OZEMPIC medicine in your pen is clear and colorless.
Look through the pen window. If OZEMPIC looks cloudy or contains particles, do not use the pen.

- Take a new needle, and tear off the paper tab.
Do not attach a new needle to your pen until you are ready to give your injection.

- Push the needle straight onto the pen. Turn until it is on tight.

- The needle is covered by 2 caps. You must remove both caps. If you forget to remove both caps, you will not inject any medicine.
- Pull off the outer needle cap. Do not throw it away.

- Pull off the inner needle cap and throw it away.
A drop of OZEMPIC may appear at the needle tip. This is normal, but you must still check the OZEMPIC flow if you use a new pen for the first time.

Always use a new needle for each injection. This will reduce the risk of contamination, infection, leakage of OZEMPIC, and blocked needles leading to the wrong dose.

Do not reuse or share your needles with other people. You may give other people a serious infection, or get a serious infection from them.

Never use a bent or damaged needle.

Step 2.

First Time Use for Each New Pen: Check the OZEMPIC flow

- Check the OZEMPIC flow before the first injection with each new pen only.
If your OZEMPIC pen is already in use, go to Step 3 “Select your dose”.
- Turn the dose selector until the dose counter shows the flow check symbol ().

- Hold the pen with the needle pointing up.
Press and hold in the dose button until the dose counter shows 0. The 0 must line up with the dose pointer.
A drop of OZEMPIC will appear at the needle tip.
- If no drop appears, repeat Step 2 above as shown in Figure G and Figure H up to 6 times. If there is still no drop, change the needle and repeat Step 2 as shown in Figure G and Figure H 1 more time.
Do not use the pen if a drop of OZEMPIC still does not appear.
Contact Novo Nordisk at 1-888-693-6742.

Always make sure that a drop appears at the needle tip before you use a new pen for the first time. This makes sure that OZEMPIC flows.

If no drop appears, you will not inject any OZEMPIC, even though the dose counter may move. This may mean that there is a blocked or damaged needle.

A small drop may remain at the needle tip, but it will not be injected.

Only check the OZEMPIC flow before your first injection with each new pen.

Step 3.

Select your dose

- Turn the dose selector until the dose counter stops and shows your 2 mg dose.

The dashed line in the dose counter will guide you to 2 mg.

Always use the dose counter and the dose pointer to see that 2 mg has been selected.

You will hear a “click” every time you turn the dose selector. Do not set the dose by counting the number of clicks you hear.

Only doses of 2 mg can be selected with the dose selector. 2 mg must line up exactly with the dose pointer to make sure that you get a correct dose.

The dose selector changes the dose. Only the dose counter and dose pointer will show that 2 mg has been selected.

You can only select 2 mg for each dose. When your pen contains less than 2 mg, the dose counter stops before 2 mg is shown.

The dose selector clicks differently when turned forward or backward. Do not count the pen clicks.

How much OZEMPIC is left?

- To see how much OZEMPIC is left in your pen, use the dose counter:
Turn the dose selector until the dose counter stops.
- If it shows 2, at least 2 mg is left in your pen. If the dose counter stops before 2 mg, there is not enough OZEMPIC left for a full dose of 2 mg.
If there is not enough OZEMPIC left in your pen for a full dose, do not use it. Use a new OZEMPIC pen.

Step 4.

Inject your dose

- Choose your injection site and wipe the skin with an alcohol swab. Let the injection site dry before you inject your dose (See Figure K).

- Insert the needle into your skin as your healthcare provider has shown you.
- Make sure you can see the dose counter. Do not cover it with your fingers. This could stop the injection.

- Press and hold down the dose button until the dose counter shows 0.
The 0 must line up with the dose pointer. You may then hear or feel a click.
Continue pressing the dose button while keeping the needle in your skin.

- Count 6 seconds while keeping the dose button pressed.
- If the needle is removed earlier, you may see a stream of OZEMPIC coming from the needle tip. If this happens, the full dose will not be delivered.

- Remove the needle from your skin. You can then release the dose button.
If blood appears at the injection site, press lightly with a gauze pad or cotton ball. Do not rub the area.

Always watch the dose counter to make sure you have injected your complete dose. Hold the dose button down until the dose counter shows 0.

How to identify a blocked or damaged needle?

- If 0 does not appear in the dose counter after continuously pressing the dose button, you may have used a blocked or damaged needle.
- If this happens you have not received any OZEMPIC even though the dose counter has moved from the original dose that you have set.

How to handle a blocked needle?

Change the needle as described in Step 5, and repeat all steps starting with Step 1: “Prepare your pen with a new needle”.

Never touch the dose counter when you inject. This can stop the injection.

You may see a drop of OZEMPIC at the needle tip after injecting. This is normal and does not affect your dose.

Step 5.

After your injection

- Carefully remove the needle from the pen. Do not put the needle caps back on the needle to avoid needle sticks.

- Place the needle in a sharps disposal container right away to reduce the risk of needle sticks. See “Disposing of used OZEMPIC pens and needles” below for more information about how to dispose of used pens and needles the right way.

- Put the pen cap on your pen after each use to protect OZEMPIC from light.

- If you do not have a sharps disposal container, follow a 1-handed needle recapping method. Carefully slip the needle into the outer needle cap. Dispose of the needle in a sharps disposal container as soon as possible.

Never try to put the inner needle cap back on the needle. You may stick yourself with the needle.

Always remove the needle from your pen.

This will reduce the risk of contamination, infection, leakage of OZEMPIC, and blocked needles leading to the wrong dose. If the needle is blocked, you will not inject any OZEMPIC.

Always dispose of the needle after each injection.

Disposing of used OZEMPIC pens and needles:

- Put your used OZEMPIC pen and needle in a FDA-cleared sharps disposal container right away after use.
- If you do not have a FDA-cleared sharps disposal container, you may use a household container that is:
  - made of a heavy-duty plastic
  - can be closed with a tight-fitting, puncture-resistant lid, without sharps being able to come out
  - upright and stable during use
  - leak-resistant
  - properly labeled to warn of hazardous waste inside the container
- When your sharps disposal container is almost full, you will need to follow your community guidelines for the right way to dispose of your sharps disposal container. There may be state or local laws about how you should throw away used needles and syringes. For more information about the safe sharps disposal, and for specific information about sharps disposal in the state that you live in, go to the FDA’s website at: http://www.fda.gov/safesharpsdisposal
- Do not dispose of your used sharps disposal container in your household trash unless your community guidelines permit this. Do not recycle your used sharps disposal container.
- Safely dispose of OZEMPIC that is out of date or no longer needed.

Important

- Caregivers must be very careful when handling used needles to prevent accidental needle stick injuries and prevent passing (transmission) of infection.
- Never use a syringe to withdraw OZEMPIC from your pen.
- Always carry an extra pen and new needles with you, in case of loss or damage.
- Always keep your pen and needles out of reach of others, especially children.
- Always keep your pen with you. Do not leave it in a car or other place where it can get too hot or too cold.

Caring for your pen

- Do not drop your pen or knock it against hard surfaces. If you drop it or suspect a problem, attach a new needle and check the OZEMPIC flow before you inject.
- Do not try to repair your pen or pull it apart.
- Do not expose your pen to dust, dirt or liquid.
- Do not wash, soak, or lubricate your pen. If necessary, clean it with mild detergent on a moistened cloth.

How should I store my OZEMPIC pen?

- Store your new, unused OZEMPIC pens in the refrigerator between 36°F to 46°F (2°C to 8°C).
- Store your pen in use for 56 days at room temperature between 59ºF to 86ºF (15ºC to 30ºC) or in a refrigerator between 36°F to 46°F (2°C to 8°C).
- The OZEMPIC pen you are using should be disposed of (thrown away) after 56 days, even if it still has OZEMPIC left in it. Write the disposal date on your calendar.
- Do not freeze OZEMPIC. Do not use OZEMPIC if it has been frozen.
- Unused OZEMPIC pens may be used until the expiration date (“EXP”) printed on the label, if kept in the refrigerator.
- When stored in the refrigerator, do not store OZEMPIC pens directly next to the cooling element.
- Keep OZEMPIC away from heat and out of the light.
- Keep the pen cap on when not in use.
- Keep OZEMPIC and all medicines out of the reach of children.

For more information go to www.OZEMPIC.com

Manufactured by:

Novo Nordisk A/S

DK-2880 Bagsvaerd

Denmark

For information about OZEMPIC contact:

Novo Nordisk Inc.

800 Scudders Mill Road

Plainsboro, NJ 08536

1-888-693-6742

Version: 2

OZEMPIC® and NovoFine® are registered trademarks of Novo Nordisk A/S.

PATENT Information: https://novonordisk-us.com/products/product-patents.html

© 2023 Novo Nordisk

This Instructions for Use has been approved by the U.S. Food and Drug Administration.

Revised: September 2023

PRINCIPAL DISPLAY PANEL – 0.25 mg or 0.5 mg doses, 2 mg/3mL

0.25 mg

0.5 mg

NDC 0169-4181-13List 418113

OZEMPIC®

(semaglutide) injection

For Single Patient Use Only

2 mg/3 mL (0.68 mg/mL) Prefilled pen

Pen delivers doses in 0.25 mg or 0.5 mg increments only

For subcutaneous use only

Use OZEMPIC once weekly

Contains: 1 OZEMPIC pen, 6 NovoFine® Plus 32G needles, Product Literature.

Dispense the enclosed Medication Guide to each patient.

PRINCIPAL DISPLAY PANEL – 1 mg dose, 4 mg/3 mL

1 mg

NDC 0169-4130-13List 413013

OZEMPIC®

(semaglutide) injection

For Single Patient Use Only

4 mg/3 mL (1.34 mg/mL) Prefilled pen

Pen delivers doses in 1 mg increments only

For subcutaneous use only

Use OZEMPIC once weekly

Contains: 1 OZEMPIC pen, 4 NovoFine® Plus 32G needles, Product Literature.

Dispense the enclosed Medication Guide to each patient.

PRINCIPAL DISPLAY PANEL – 2 mg dose, 8mg/3 mL

2 mg

NDC 0169-4772-12List 477212

OZEMPIC®

(semaglutide) injection

For Single Patient Use Only

8 mg/3 mL (2.68 mg/mL) Prefilled pen

Pen delivers 4 doses of 2 mg only

For subcutaneous use only

Use OZEMPIC once weekly

Contains: 1 OZEMPIC pen, 4 NovoFine® Plus 32G needles, Product Literature.

Dispense the enclosed Medication Guide to each patient.

PACKAGE/LABEL PRINCIPAL DISPLAY PANEL – 0.25 mg and 0/5 mg, 1.5 mL

0.25 mg

0.5 mg

NDC 0169-4132-12List 413212

OZEMPIC®

(semaglutide) injection

For Single Patient Use Only

2 mg/1.5 mL (1.34 mg/mL) Prefilled pen

Pen delivers doses in 0.25 mg or 0.5 mg increments only

For subcutaneous use only

Use OZEMPIC once weekly

Contains: 1 OZEMPIC pen, 6 NovoFine® Plus 32G needles, Product Literature.

Dispense the enclosed Medication Guide to each patient.

PACKAGE/LABEL PRINCIPAL DISPLAY PANEL – 1 mg, 1.5 mL

1 mg

NDC 0169-4136-02List 413602

OZEMPIC®

(semaglutide) injection

For Single Patient Use Only

2 mg/1.5 mL (1.34 mg/mL) Prefilled pen

Pen delivers doses in 1 mg increments only

For subcutaneous use only

Use OZEMPIC once weekly

Contains: 2 OZEMPIC pens, 4 NovoFine® Plus 32G needles, Product Literature.

Dispense the enclosed Medication Guide to each patient.